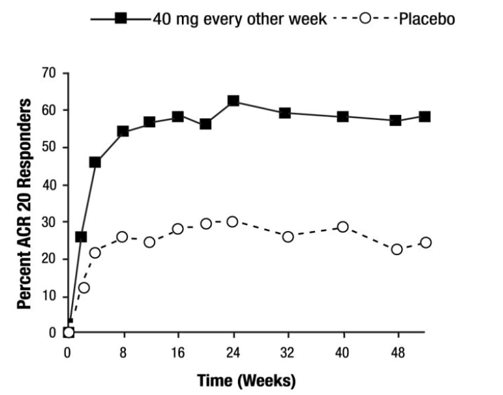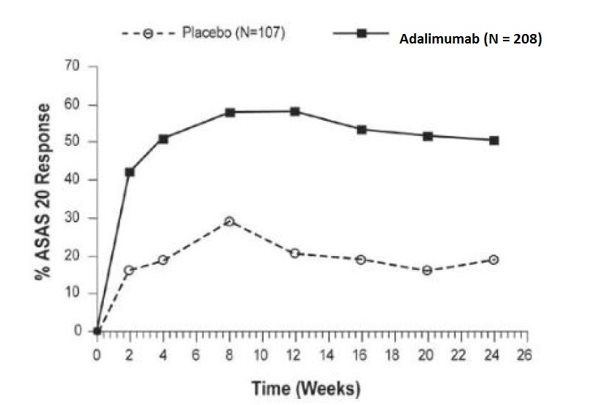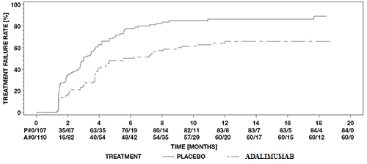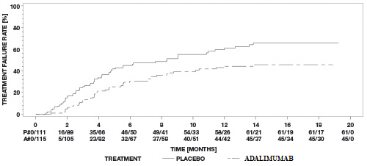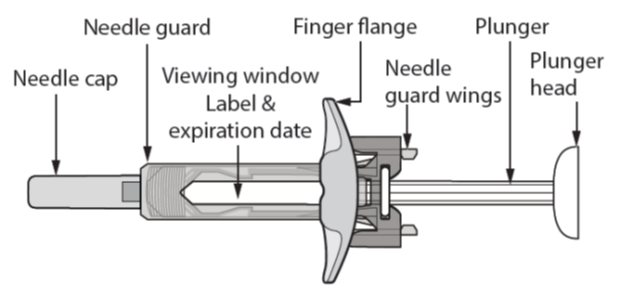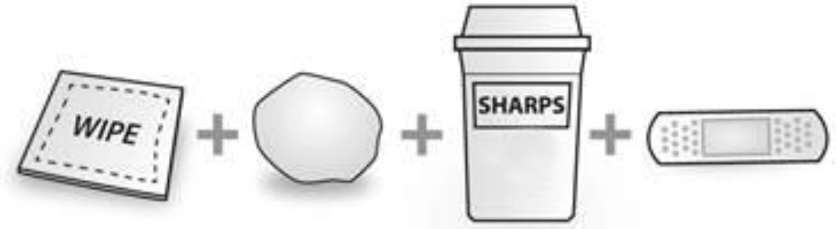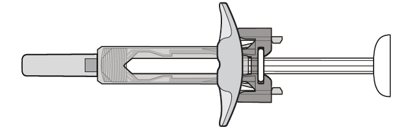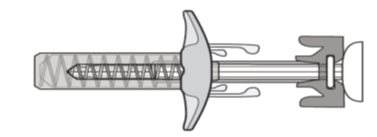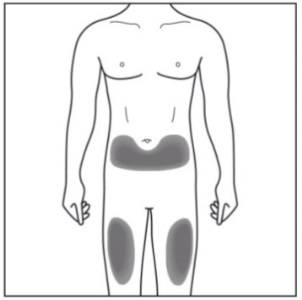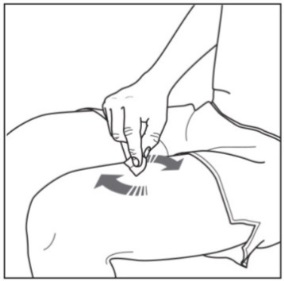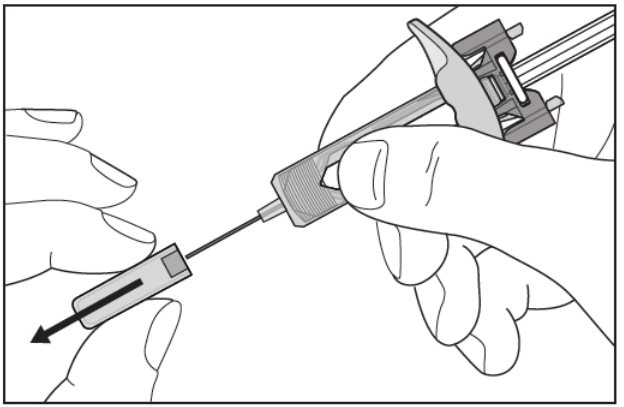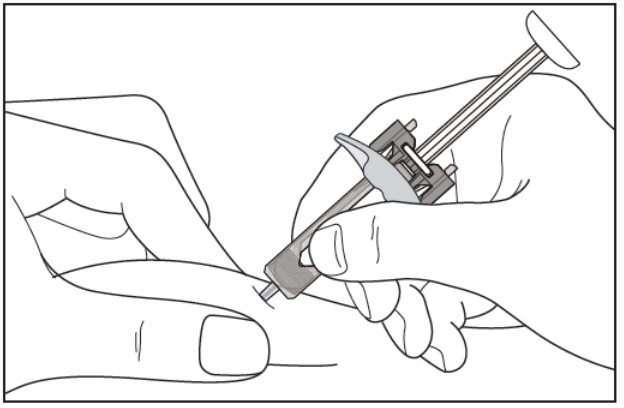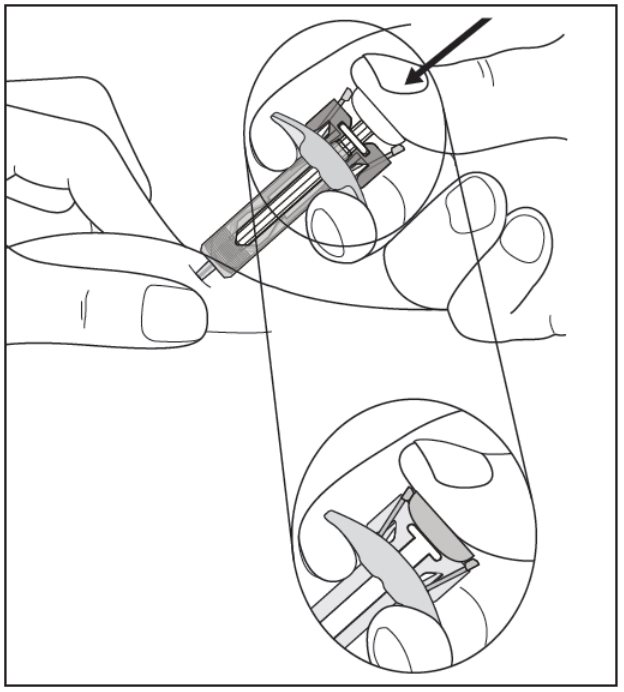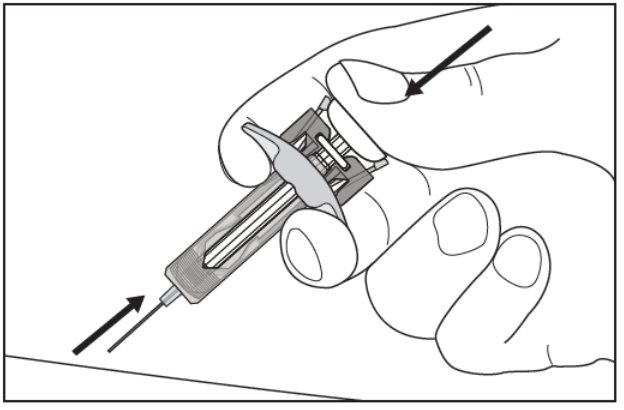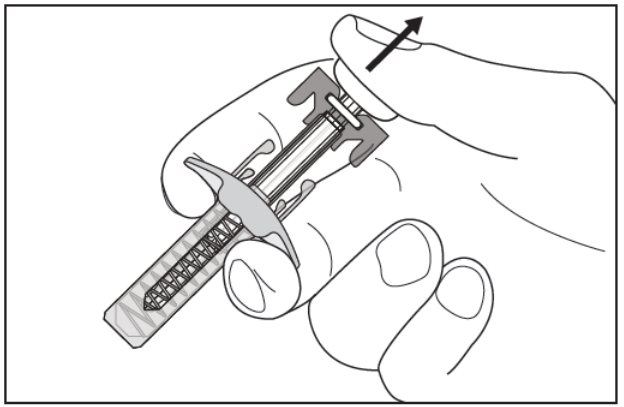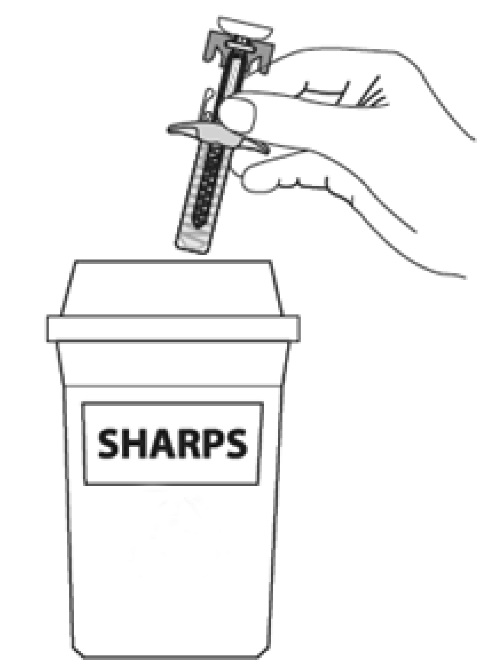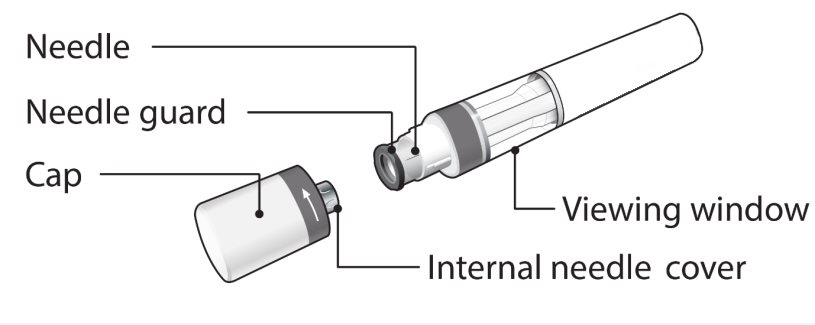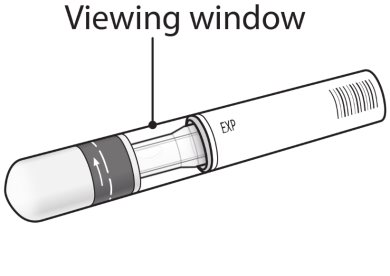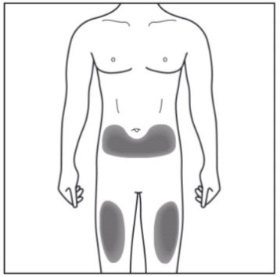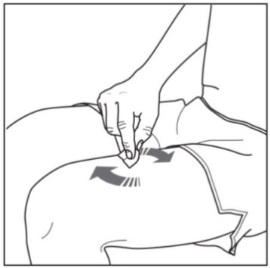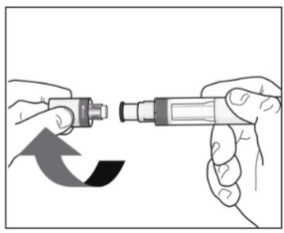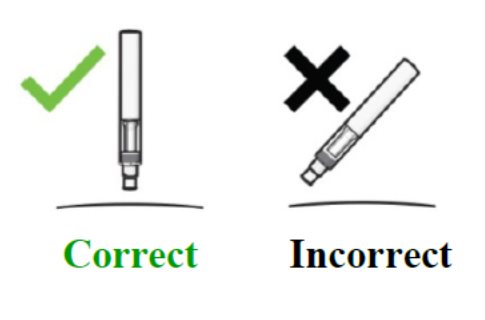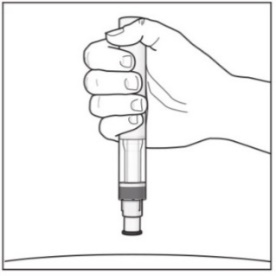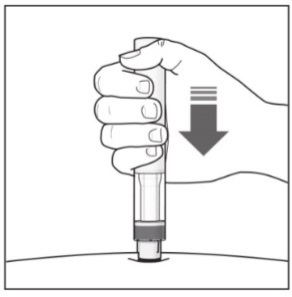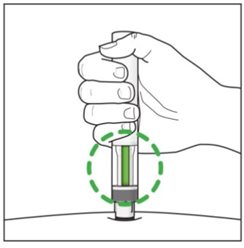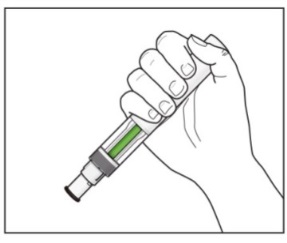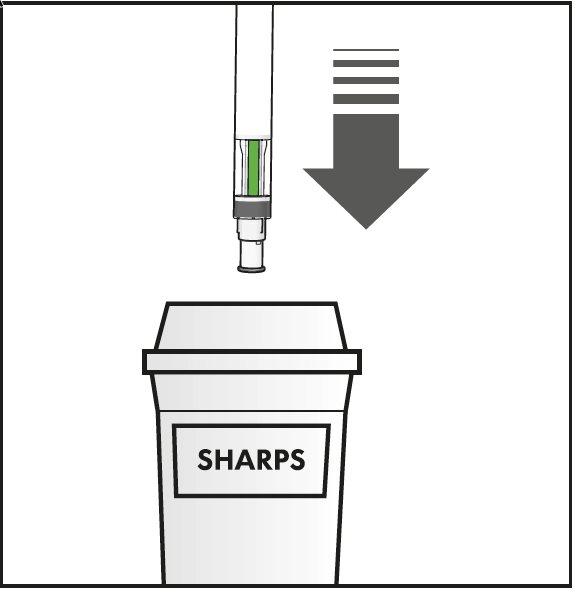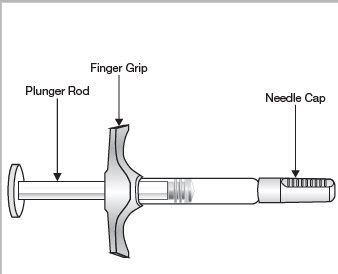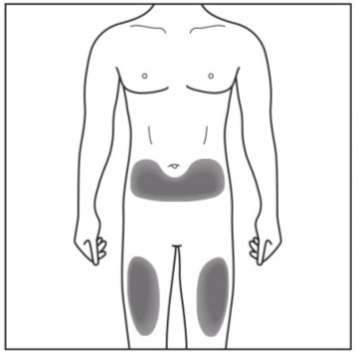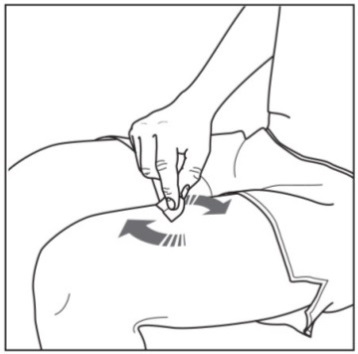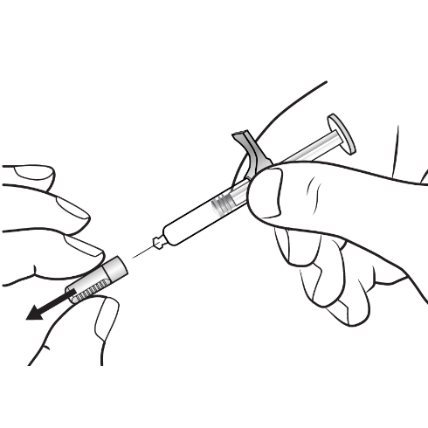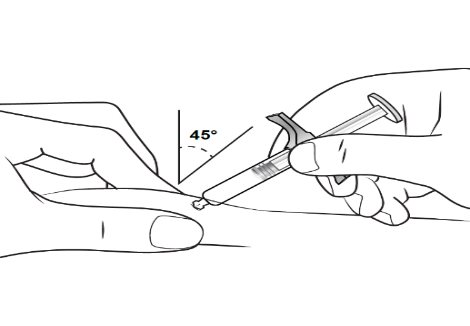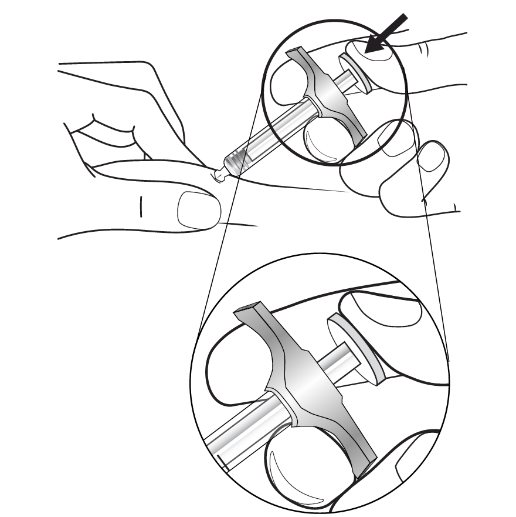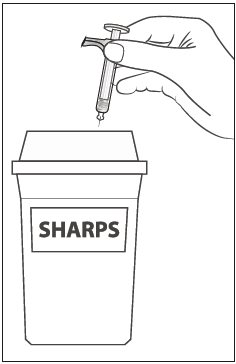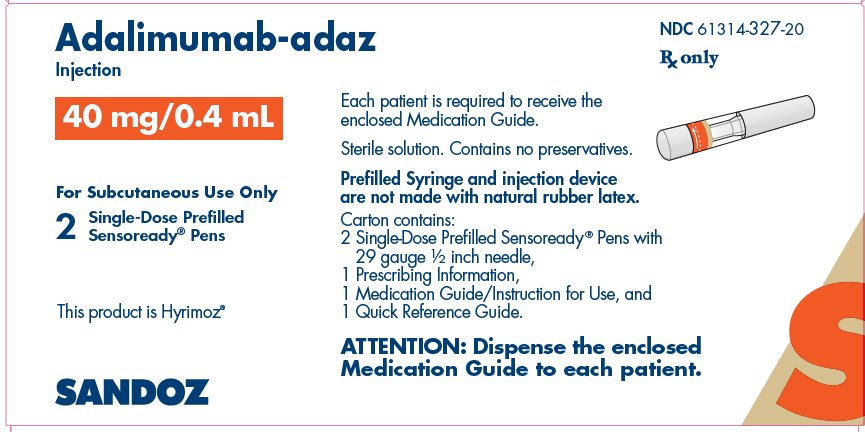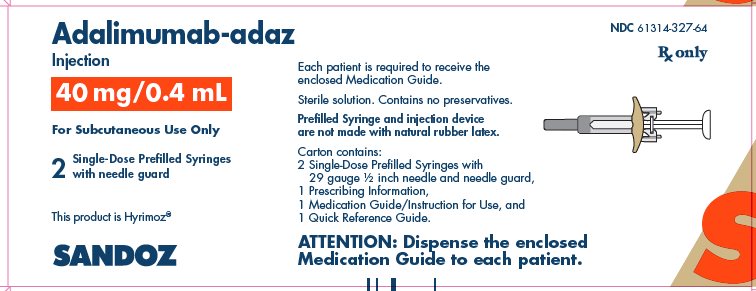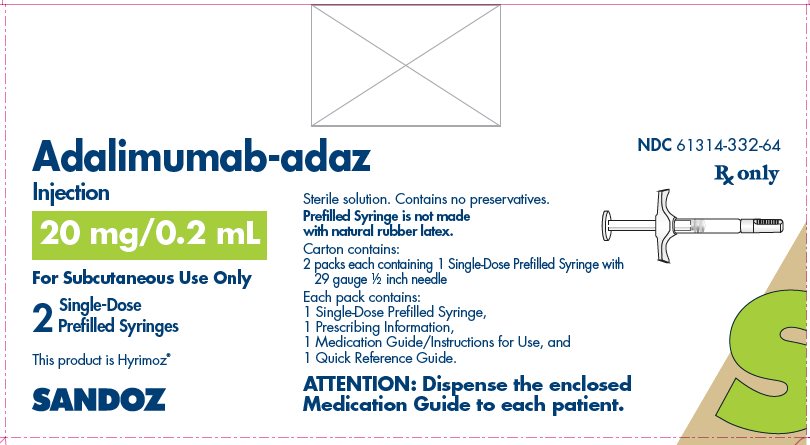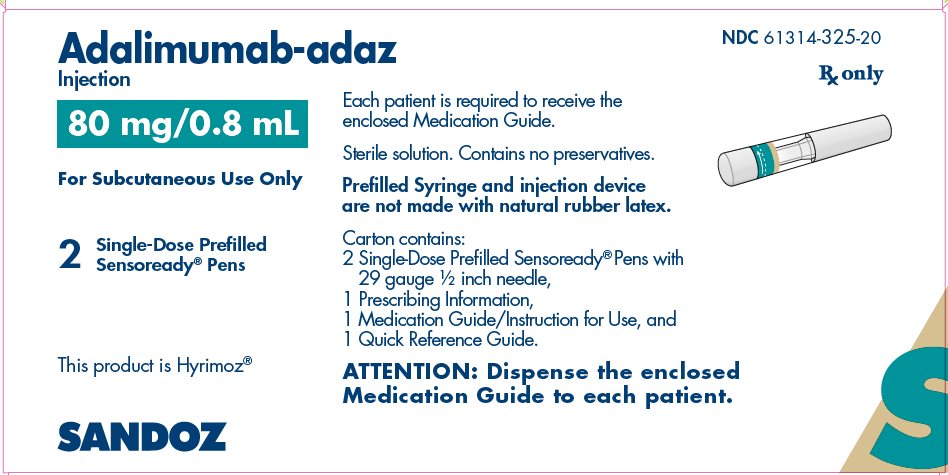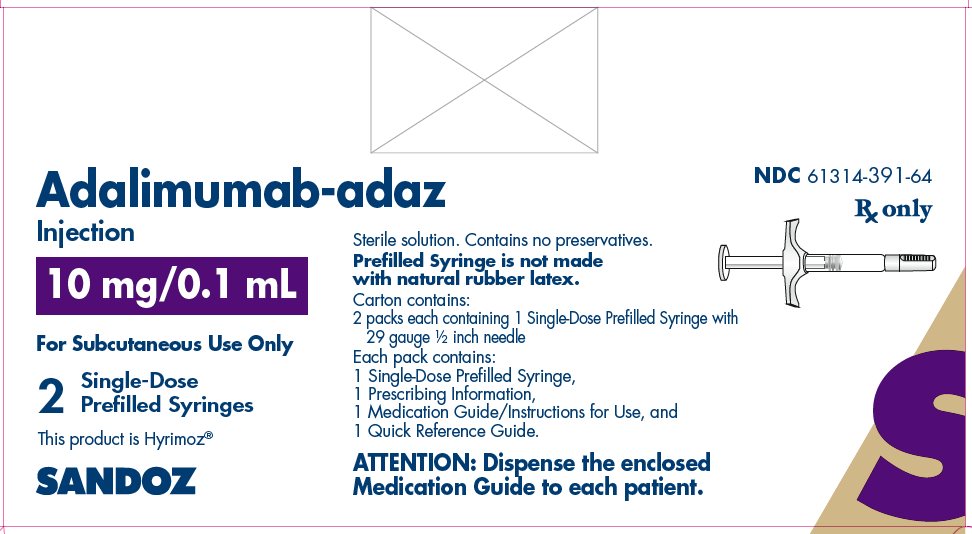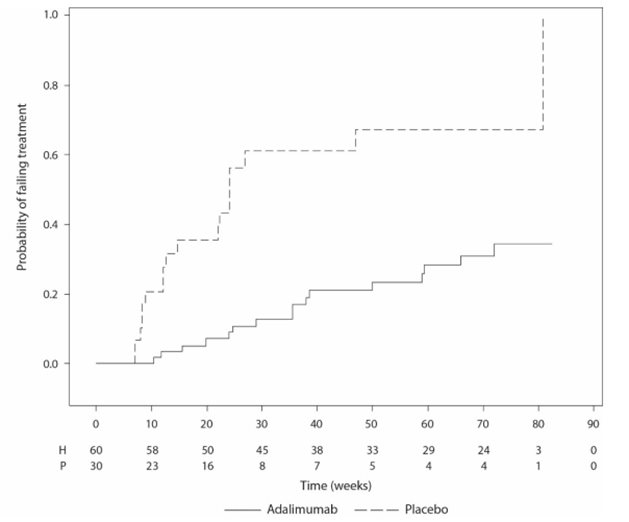 DRUG LABEL: Adalimumab
NDC: 61314-327 | Form: INJECTION, SOLUTION
Manufacturer: Sandoz Inc
Category: prescription | Type: HUMAN PRESCRIPTION DRUG LABEL
Date: 20251021

ACTIVE INGREDIENTS: ADALIMUMAB 40 mg/0.4 mL
INACTIVE INGREDIENTS: ADIPIC ACID 0.88 mg/0.4 mL; MANNITOL 16.8 mg/0.4 mL; POLYSORBATE 80 0.16 mg/0.4 mL; WATER; HYDROCHLORIC ACID; SODIUM HYDROXIDE

HIGHLIGHTS OF PRESCRIBING INFORMATION

These highlights do not include all the information needed to use ADALIMUMAB-ADAZ safely and effectively. See full prescribing information for ADALIMUMAB-ADAZ.
ADALIMUMAB-ADAZ injection, for subcutaneous use
Initial U.S. Approval: 2018
This product is HYRIMOZ (adalimumab-adaz). HYRIMOZ (adalimumab-adaz) is biosimilar* to HUMIRA® (adalimumab).

RECENT MAJOR CHANGES

Indications and Usage, Hidradenitis Suppurativa (1.8) 10/2025

Indications and Usage, Uveitis (1.9) 10/2025

Dosage and Administration, Uveitis (2.3) 10/2025

Dosage and Administration, Hidradenitis Suppurativa (2.7) 10/2025

Warnings and Precautions, Autoimmunity (5.9) 10/2025

WARNING: SERIOUS INFECTIONS and MALIGNANCY

See full prescribing information for complete boxed warning.

SERIOUS INFECTIONS (5.1, 6.1):

- Increased risk of serious infections leading to hospitalization or death, including tuberculosis (TB), bacterial sepsis, invasive fungal infections (such as histoplasmosis), and infections due to other opportunistic pathogens.
- Discontinue Adalimumab-adaz if a patient develops a serious infection or sepsis during treatment.
- Perform test for latent TB; if positive, start treatment for TB prior to starting Adalimumab-adaz.
- Monitor all patients for active TB during treatment, even if initial latent TB test is negative.

MALIGNANCY (5.2):

- Lymphoma and other malignancies, some fatal, have been reported in children and adolescent patients treated with TNF blockers including adalimumab products.
- Post-marketing cases of hepatosplenic T-cell lymphoma (HSTCL), a rare type of T-cell lymphoma, have occurred in adolescent and young adults with inflammatory bowel disease treated with TNF blockers including adalimumab products.

1 INDICATIONS AND USAGE

Adalimumab-adaz is a tumor necrosis factor (TNF)-blocker indicated for:

- Reducing signs and symptoms, inducing major clinical response, inhibiting the progression of structural damage, and improving physical function in adult patients with moderately to severely active rheumatoid arthritis. (1.1)
- Reducing signs and symptoms of moderately to severely active polyarticular juvenile idiopathic arthritis in patients 2 years of age and older. (1.2)
- Reducing signs and symptoms, inhibiting the progression of structural damage, and improving physical function in adult patients with active psoriatic arthritis. (1.3)
- Reducing signs and symptoms in adult patients with active ankylosing spondylitis. (1.4)
- Treatment of moderately to severely active Crohn’s disease in adults and pediatric patients 6 years of age and older. (1.5)
- Treatment of moderately to severely active ulcerative colitis in adult patients. (1.6)
Limitations of Use: Effectiveness has not been established in patients who have lost response to or were intolerant to TNF blockers.
- Treatment of adult patients with moderate to severe chronic plaque psoriasis who are candidates for systemic therapy or phototherapy, and when other systemic therapies are medically less appropriate. (1.7)
- Treatment of moderate to severe hidradenitis suppurativa in patients 12 years of age and older. (1.8)
- Treatment of non-infectious intermediate, posterior, and panuveitis in adults and pediatric patients 2 years of age and older. (1.9)

2 DOSAGE AND ADMINISTRATION

- Administer by subcutaneous injection (2)

Rheumatoid Arthritis, Psoriatic Arthritis, Ankylosing Spondylitis (2.2):

- Adults: 40 mg every other week.

Some patients with RA not receiving methotrexate may benefit from increasing the dosage to 40 mg every week or 80 mg every other week.

Juvenile Idiopathic Arthritis or Pediatric Uveitis (2.3):

Pediatric Weight; 2 Years of Age and Older | Recommended Dosage
10 kg (22 lbs) to less than 15 kg (33 lbs) | 10 mg every other week
15 kg (33 lbs) to less than 30 kg (66 lbs) | 20 mg every other week
30 kg (66 lbs) and greater | 40 mg every other week

Crohn's Disease (2.4):

- Adults: 160 mg on Day 1 (given in one day or split over two consecutive days); 80 mg on Day 15; and 40 mg
every other week starting on Day 29.
- Pediatric Patients 6 Years of Age and Older:

Pediatric Weight | Recommended Dosage
Pediatric Weight | Days 1 and 15 | Starting on Day 29
17 kg (37 lbs) to less than 40 kg (88 lbs) | Day 1: 80 mg; Day 15: 40 mg | 20 mg every other week
40 kg (88 lbs) and greater | Day 1: 160 mg (single dose or split over two consecutive days); Day 15: 80 mg | 40 mg every other week

Ulcerative Colitis (2.5):

- Adults: 160 mg on Day 1 (given in one day or split over two consecutive days), 80 mg on Day 15 and 40 mg every other week starting on Day 29.
Discontinue in patients without evidence of clinical remission by eight weeks (Day 57).

Plaque Psoriasis or Adult Uveitis (2.6):

- Adults: 80 mg initial dose, followed by 40 mg every other week starting one week after initial dose.

Hidradenitis Suppurativa (2.7):

- Adults:
- Day 1: 160 mg (given in one day or split over two consecutive days)
- Day 15: 80 mg
- Day 29 and subsequent doses: 40 mg every week or 80 mg every other week
- Adolescents 12 years of age and older:

Adolescent Weight | Recommended Dosage
30 kg (66 lbs) to less than 60 kg (132 lbs) | Day 1: 80 mg; Day 8 and subsequent doses: 40 mg every other week
60 kg (132 lbs) and greater | Day 1: 160 mg (given in one day or split over two consecutive days); Day 15: 80 mg; Day 29 and subsequent doses: 40 mg every week or 80 mg every other week

3 DOSAGE FORMS AND STRENGTHS

Injection:

- Single-dose prefilled pen (Sensoready Pen): 40 mg/0.4 mL and 80 mg/0.8 mL (3)
- Single-dose prefilled glass syringe (with BD UltraSafe Passive™ Needle Guard): 40 mg/0.4 mL and 80 mg/0.8 mL (3)
- Single-dose prefilled glass syringe: 10 mg/0.1 mL and 20 mg/0.2 mL (3)

4 CONTRAINDICATIONS

None (4)

5 WARNINGS AND PRECAUTIONS

- Serious infections: Do not start Adalimumab-adaz during an active infection. If an infection develops, monitor carefully, and stop Adalimumab-adaz if infection becomes serious. (5.1)
- Invasive fungal infections: For patients who develop a systemic illness on Adalimumab-adaz, consider empiric antifungal therapy for those who reside or travel to regions where mycoses are endemic. (5.1)
- Malignancies: Incidence of malignancies was greater in adalimumab-treated patients than in controls. (5.2)
- Anaphylaxis or serious hypersensitivity reactions may occur. (5.3)
- Hepatitis B virus reactivation: Monitor HBV carriers during and several months after therapy. If reactivation occurs, stop Adalimumab-adaz and begin anti-viral therapy. (5.4)
- Demyelinating disease: Exacerbation or new onset, may occur. (5.5)
- Cytopenias, pancytopenia: Advise patients to seek immediate medical attention if symptoms develop, and consider stopping Adalimumab-adaz. (5.6)
- Heart failure: Worsening or new onset, may occur. (5.8)
- Autoimmunity: Stop Adalimumab-adaz if lupus-like syndrome or autoimmune hepatitis develop. (5.9)

6 ADVERSE REACTIONS

Most common adverse reactions (>10%) are: infections (e.g. upper respiratory, sinusitis), injection site reactions, headache and rash (6.1)

To report SUSPECTED ADVERSE REACTIONS, contact Sandoz Inc. at 1-800-525-8747 or FDA at 1-800-FDA-1088 or www.fda.gov/medwatch

7 DRUG INTERACTIONS

- Abatacept: Increased risk of serious infection (5.1, 5.11, 7.2)
- Anakinra: Increased risk of serious infection (5.1, 5.7, 7.2)
- Live vaccines: Avoid use with Adalimumab-adaz (5.10, 7.3)

* Biosimilar means that the biological product is approved based on data demonstrating that it is highly similar to an FDA-approved biological product, known as a reference product, and that there are no clinically meaningful differences between the biosimilar product and the reference product. Biosimilarity of Adalimumab-adaz has been demonstrated for the condition(s) of use (e.g. indication(s), dosing regimen(s)), strength(s), dosage form(s), and route(s) of administration described in its Full Prescribing Information.

FULL PRESCRIBING INFORMATION

WARNING: SERIOUS INFECTIONS and MALIGNANCY

SERIOUS INFECTIONS

Patients treated with adalimumab products, including Adalimumab-adaz, are at increased risk for developing serious infections that may lead to hospitalization or death [see Warnings and Precautions (5.1)]. Most patients who developed these infections were taking concomitant immunosuppressants such as methotrexate or corticosteroids.

Discontinue Adalimumab-adaz if a patient develops a serious infection or sepsis.

Reported infections include:

- Active tuberculosis (TB), including reactivation of latent TB. Patients with TB have frequently presented with disseminated or extrapulmonary disease. Test patients for latent TB before Adalimumab-adaz use and during therapy. Initiate treatment for latent TB prior to Adalimumab-adaz use.
- Invasive fungal infections, including histoplasmosis, coccidioidomycosis, candidiasis, aspergillosis, blastomycosis, and pneumocystosis. Patients with histoplasmosis or other invasive fungal infections may present with disseminated, rather than localized, disease. Antigen and antibody testing for histoplasmosis may be negative in some patients with active infection. Consider empiric anti-fungal therapy in patients at risk for invasive fungal infections who develop severe systemic illness.
- Bacterial, viral and other infections due to opportunistic pathogens, including Legionella and Listeria.

Carefully consider the risks and benefits of treatment with Adalimumab-adaz prior to initiating therapy in patients with chronic or recurrent infection.

Monitor patients closely for the development of signs and symptoms of infection during and after treatment with Adalimumab-adaz, including the possible development of TB in patients who tested negative for latent TB infection prior to initiating therapy [see Warnings and Precautions (5.1) and Adverse Reactions (6.1)].

MALIGNANCY

Lymphoma and other malignancies, some fatal, have been reported in children and adolescent patients treated with TNF blockers including adalimumab products [see Warnings and Precautions (5.2)]. Post-marketing cases of hepatosplenic T-cell lymphoma (HSTCL), a rare type of T-cell lymphoma, have been reported in patients treated with TNF blockers including adalimumab products. These cases have had a very aggressive disease course and have been fatal. The majority of reported TNF blocker cases have occurred in patients with Crohn's disease or ulcerative colitis and the majority were in adolescent and young adult males. Almost all these patients had received treatment with azathioprine or 6-mercaptopurine (6–MP) concomitantly with a TNF blocker at or prior to diagnosis. It is uncertain whether the occurrence of HSTCL is related to use of a TNF blocker or a TNF blocker in combination with these other immunosuppressants [see Warnings and Precautions (5.2)].

1 INDICATIONS AND USAGE

1.1 Rheumatoid Arthritis

Adalimumab-adaz is indicated for reducing signs and symptoms, inducing major clinical response, inhibiting the progression of structural damage, and improving physical function in adult patients with moderately to severely active rheumatoid arthritis. Adalimumab-adaz can be used alone or in combination with methotrexate or other non-biologic disease-modifying anti-rheumatic drugs (DMARDs).

1.2 Juvenile Idiopathic Arthritis

Adalimumab-adaz is indicated for reducing signs and symptoms of moderately to severely active polyarticular juvenile idiopathic arthritis in patients 2 years of age and older. Adalimumab-adaz can be used alone or in combination with methotrexate.

1.3 Psoriatic Arthritis

Adalimumab-adaz is indicated for reducing signs and symptoms, inhibiting the progression of structural damage, and improving physical function in adult patients with active psoriatic arthritis. Adalimumab-adaz can be used alone or in combination with non-biologic DMARDs.

1.4 Ankylosing Spondylitis

Adalimumab-adaz is indicated for reducing signs and symptoms in adult patients with active ankylosing spondylitis.

1.5 Crohn’s Disease

Adalimumab-adaz is indicated for the treatment of moderately to severely active Crohn’s disease in adults and pediatric patients 6 years of age and older.

1.6 Ulcerative Colitis

Adalimumab-adaz is indicated for the treatment of moderately to severely active ulcerative colitis in adult patients.

Limitations of Use:

The effectiveness of adalimumab products has not been established in patients who have lost response to or were intolerant to TNF-blockers [see Clinical Studies (14.7)].

1.7 Plaque Psoriasis

Adalimumab-adaz is indicated for the treatment of adult patients with moderate to severe chronic plaque psoriasis who are candidates for systemic therapy or phototherapy, and when other systemic therapies are medically less appropriate. Adalimumab-adaz should only be administered to patients who will be closely monitored and have regular follow-up visits with a physician [see Warnings and Precautions (5)].

1.8 Hidradenitis Suppurativa

Adalimumab-adaz is indicated for the treatment of moderate to severe hidradenitis suppurativa in patients 12 years of age and older.

1.9 Uveitis

Adalimumab-adaz is indicated for the treatment of non-infectious intermediate, posterior, and panuveitis in adults and pediatric patients 2 years of age and older.

2 DOSAGE AND ADMINISTRATION

2.1 Recommended Tuberculosis Evaluation

Prior to initiating Adalimumab-adaz and periodically during therapy, evaluate patients for active tuberculosis and test for latent infection [see Warnings and Precautions (5.1)].

2.2 Recommended Dosage in Rheumatoid Arthritis, Psoriatic Arthritis, and Ankylosing Spondylitis

The recommended subcutaneous dosage of Adalimumab-adaz for adult patients with rheumatoid arthritis (RA), psoriatic arthritis (PsA), or ankylosing spondylitis (AS) [see Indication and Usage (1.1, 1.3, 1.4)] is 40 mg administered every other week. Methotrexate (MTX), other non-biologic DMARDs, glucocorticoids, nonsteroidal anti-inflammatory drugs (NSAIDs), and/or analgesics may be continued during treatment with Adalimumab-adaz. In the treatment of RA, some patients not taking concomitant MTX may derive additional benefit from increasing the dosage of Adalimumab-adaz to 40 mg every week or 80 mg every other week.

2.3 Recommended Dosage in Juvenile Idiopathic Arthritis or Pediatric Patients with Uveitis

The recommended subcutaneous dosage of Adalimumab-adaz for pediatric patients 2 years of age and older with polyarticular juvenile idiopathic arthritis (JIA) or pediatric uveitis [see Indications and Usage (1.2, 1.9)], based on weight, is shown below. MTX, glucocorticoids, NSAIDs, and/or analgesics may be continued during treatment with Adalimumab-adaz.

Pediatric Weight (2 Years of Age and older) | Recommended Dosage
10 kg (22 lbs) to less than 15 kg (33 lbs) | 10 mg every other week
15 kg (33 lbs) to less than 30 kg (66 lbs) | 20 mg every other week
30 kg (66 lbs) and greater | 40 mg every other week

Adalimumab products have not been studied in patients with polyarticular JIA or pediatric uveitis less than 2 years of age or in patients with a weight below 10 kg.

2.4 Recommended Dosage in Crohn’s Disease

Subcutaneous Adult Dosage Regimen

The recommended subcutaneous dosage of Adalimumab-adaz for adult patients with moderately to severely active Crohn’s disease (CD) is 160 mg initially on Day 1 (given in one day or split over two consecutive days), followed by 80 mg two weeks later (Day 15). Two weeks later (Day 29) begin a dosage of 40 mg every other week. Aminosalicylates and/or corticosteroids may be continued during treatment with Adalimumab-adaz. Azathioprine, 6-mercaptopurine (6-MP) [see Warnings and Precautions (5.2)] or MTX may be continued during treatment with Adalimumab-adaz if necessary.

Subcutaneous Pediatric Dosage Regimen

The recommended subcutaneous dosage of Adalimumab-adaz for pediatric patients 6 years of age and older with moderately to severely active Crohn’s disease (CD), based on body weight, is shown below:

Pediatric Weight | Recommended Dosage
Pediatric Weight | Days 1 through 15 | Starting on Day 29
17 kg (37 lbs) to less than 40 kg (88 lbs) | Day 1: 80 mg; Day 15: 40 mg | 20 mg every other week
40 kg (88 lbs) and greater | Day 1: 160 mg (single dose or split over two consecutive days); Day 15: 80 mg | 40 mg every other week

2.5 Recommended Dosage in Ulcerative Colitis

Subcutaneous Adult Dosage Regimen

The recommended subcutaneous dosage of Adalimumab-adaz for adult patients with moderately to severely active ulcerative colitis is 160 mg initially on Day 1 (given in one day or split over two consecutive days), followed by 80 mg two weeks later (Day 15). Two weeks later (Day 29) continue with a dosage of 40 mg every other week.

Discontinue Adalimumab-adaz in adult patients without evidence of clinical remission by eight weeks (Day 57) of therapy. Aminosalicylates and/or corticosteroids may be continued during treatment with Adalimumab-adaz. Azathioprine and 6-mercaptopurine (6-MP) [see Warnings and Precautions (5.2)] may be continued during treatment with Adalimumab-adaz if necessary.

2.6 Recommended Dosage in Plaque Psoriasis or Adults with Uveitis

The recommended subcutaneous dosage of Adalimumab-adaz for adult patients with plaque psoriasis (Ps) or uveitis (UV) [see Indications and Usage (1.7, 1.9)] is an initial dose of 80 mg, followed by 40 mg given every other week starting one week after the initial dose. The use of adalimumab products in moderate to severe chronic Ps beyond one year has not been evaluated in controlled clinical studies.

2.7 Recommended Dosage in Hidradenitis Suppurativa

Subcutaneous Adult Dosage Regimen

The recommended subcutaneous dosage of Adalimumab-adaz for adult patients with moderate to severe hidradenitis suppurativa (HS) is an initial dose of 160 mg (given in one day or split over two consecutive days), followed by 80 mg two weeks later (Day 15). Begin 40 mg weekly or 80 mg every other week dosing two weeks later (Day 29).

Subcutaneous Pediatric Dosage Regimen

The recommended subcutaneous dosage of Adalimumab-adaz for pediatric patients 12 years of age and older weighing at least 30 kg with moderate to severe hidradenitis suppurativa (HS), based on body weight, is shown below [see Use in Specific Populations (8.4) and Clinical Pharmacology (12.3)]:

Body Weight of Pediatric Patients (12 years of age and older) | Recommended Dosage
30 kg (66 lbs) to less than 60 kg (132 lbs) | - Day 1: 80 mg - Day 8 and subsequent doses: 40 mg every other week
60 kg (132 lbs) and greater | - Day 1: 160 mg (given in one day or split over two consecutive days); - Day 15: 80 mg - Day 29 and subsequent doses: 40 mg every week or 80 mg every other week

2.8 General Considerations for Administration

Adalimumab-adaz is intended for use under the guidance and supervision of a physician. A patient may self-inject Adalimumab-adaz or a caregiver may inject Adalimumab-adaz using either the Adalimumab-adaz single-dose prefilled Sensoready Pen or the Adalimumab-adaz single-dose prefilled syringe if a physician determines that it is appropriate, and with medical follow-up, as necessary, after proper training in subcutaneous injection technique.

Adalimumab-adaz can be taken out of the refrigerator for 15 to 30 minutes before injecting to allow the liquid to come to room temperature. Do not remove the cap while allowing it to reach room temperature. Carefully inspect the solution in the Adalimumab-adaz single-dose prefilled Sensoready Pen or Adalimumab-adaz single-dose prefilled syringe for particulate matter and discoloration prior to subcutaneous administration. The solution should be clear, colorless or slightly yellowish. Do not use a prefilled syringe or prefilled Sensoready Pen if the solution is cloudy, discolored, or has flakes or particles in it. Adalimumab-adaz does not contain preservatives; therefore, discard unused portions of drug remaining from the syringe.

Instruct patients using the Adalimumab-adaz single-dose prefilled Sensoready Pen and the Adalimumab-adaz single-dose prefilled syringe to inject the full amount according to the directions provided in the Instructions for Use [see Instructions for Use].

Injections should occur at separate sites in the thigh or abdomen. Rotate injection sites and do not give injections into areas where the skin is tender, bruised, red or hard.

If a dose is missed, administer the dose as soon as possible. Thereafter, resume dosing at the regular scheduled time.

3 DOSAGE FORMS AND STRENGTHS

Adalimumab-adaz is a clear, colorless or slightly yellowish solution available as:

- Pen (Sensoready Pen)
Injection: 80 mg/0.8 mL in a single-dose pen.
Injection: 40 mg/0.4 mL in a single-dose pen.
- Prefilled Syringe with BD UltraSafe Passive™ Needle Guard
Injection: 80 mg/0.8 mL in a single-dose prefilled glass syringe.
Injection: 40 mg/0.4 mL in a single-dose prefilled glass syringe.
- Prefilled Syringe
Injection: 20 mg/0.2 mL in a single-dose prefilled glass syringe.
Injection: 10 mg/0.1 mL in a single-dose prefilled glass syringe.

4 CONTRAINDICATIONS

None.

5 WARNINGS AND PRECAUTIONS

5.1 Serious Infections

Patients treated with adalimumab products, including Adalimumab-adaz, are at increased risk for developing serious infections involving various organ systems and sites that may lead to hospitalization or death. Opportunistic infections due to bacterial, mycobacterial, invasive fungal, viral, parasitic, or other opportunistic pathogens including aspergillosis, blastomycosis, candidiasis, coccidioidomycosis, histoplasmosis, legionellosis, listeriosis, pneumocystosis and tuberculosis have been reported with TNF blockers. Patients have frequently presented with disseminated rather than localized disease.

The concomitant use of a TNF blocker and abatacept or anakinra was associated with a higher risk of serious infections in patients with rheumatoid arthritis (RA); therefore, the concomitant use of Adalimumab-adaz and these biologic products is not recommended in the treatment of patients with RA [see Warnings and Precautions (5.7, 5.11) and Drug Interactions (7.2)].

Treatment with Adalimumab-adaz should not be initiated in patients with an active infection, including localized infections. Patients 65 years of age and older, patients with co-morbid conditions and/or patients taking concomitant immunosuppressants (such as corticosteroids or methotrexate), may be at greater risk of infection. Consider the risks and benefits of treatment prior to initiating therapy in patients:

- with chronic or recurrent infection;
- who have been exposed to tuberculosis;
- with a history of an opportunistic infection;
- who have resided or traveled in areas of endemic tuberculosis or endemic mycoses, such as histoplasmosis, coccidioidomycosis, or blastomycosis; or
- with underlying conditions that may predispose them to infection.

Tuberculosis

Cases of reactivation of tuberculosis and new onset tuberculosis infections have been reported in patients receiving adalimumab products, including patients who have previously received treatment for latent or active tuberculosis. Reports included cases of pulmonary and extrapulmonary (i.e., disseminated) tuberculosis. Evaluate patients for tuberculosis risk factors and test for latent infection prior to initiating Adalimumab-adaz and periodically during therapy.

Treatment of latent tuberculosis infection prior to therapy with TNF blocking agents has been shown to reduce the risk of tuberculosis reactivation during therapy. Prior to initiating Adalimumab-adaz, assess if treatment for latent tuberculosis is needed; and consider an induration of ≥ 5 mm a positive tuberculin skin test result, even for patients previously vaccinated with Bacille Calmette-Guerin (BCG).

Consider anti-tuberculosis therapy prior to initiation of Adalimumab-adaz in patients with a past history of latent or active tuberculosis in whom an adequate course of treatment cannot be confirmed, and for patients with a negative test for latent tuberculosis but having risk factors for tuberculosis infection. Despite prophylactic treatment for tuberculosis, cases of reactivated tuberculosis have occurred in patients treated with adalimumab products. Consultation with a physician with expertise in the treatment of tuberculosis is recommended to aid in the decision whether initiating anti-tuberculosis therapy is appropriate for an individual patient.

Strongly consider tuberculosis in the differential diagnosis in patients who develop a new infection during Adalimumab-adaz treatment, especially in patients who have previously or recently traveled to countries with a high prevalence of tuberculosis, or who have had close contact with a person with active tuberculosis.

Monitoring

Closely monitor patients for the development of signs and symptoms of infection during and after treatment with Adalimumab-adaz, including the development of tuberculosis in patients who tested negative for latent tuberculosis infection prior to initiating therapy. Tests for latent tuberculosis infection may also be falsely negative while on therapy with Adalimumab-adaz.

Discontinue Adalimumab-adaz if a patient develops a serious infection or sepsis. For a patient who develops a new infection during treatment with Adalimumab-adaz, closely monitor them, perform a prompt and complete diagnostic workup appropriate for an immunocompromised patient, and initiate appropriate antimicrobial therapy.

Invasive Fungal Infections

If patients develop a serious systemic illness and they reside or travel in regions where mycoses are endemic, consider invasive fungal infection in the differential diagnosis. Antigen and antibody testing for histoplasmosis may be negative in some patients with active infection. Consider appropriate empiric antifungal therapy, taking into account both the risk for severe fungal infection and the risks of antifungal therapy, while a diagnostic workup is being performed. To aid in the management of such patients, consider consultation with a physician with expertise in the diagnosis and treatment of invasive fungal infections.

5.2 Malignancies

Consider the risks and benefits of TNF-blocker treatment including Adalimumab-adaz prior to initiating therapy in patients with a known malignancy other than a successfully treated non-melanoma skin cancer (NMSC) or when considering continuing a TNF-blocker in patients who develop a malignancy.

Malignancies in Adults

In the controlled portions of clinical trials of some TNF-blockers, including adalimumab products, more cases of malignancies have been observed among TNF-blocker-treated adult subjects compared to control-treated adult subjects. During the controlled portions of 39 global adalimumab clinical trials in adult patients with rheumatoid arthritis (RA), psoriatic arthritis (PsA), ankylosing spondylitis (AS), Crohn’s disease (CD), ulcerative colitis (UC), plaque psoriasis (Ps), hidradenitis suppurativa (HS) and uveitis (UV), malignancies, other than non-melanoma (basal cell and squamous cell) skin cancer, were observed at a rate (95% confidence interval) of 0.7 (0.48, 1.03) per 100 patient-years among 7973 adalimumab-treated subjects versus a rate of 0.7 (0.41, 1.17) per 100 patient-years among 4848 control-treated subjects (median duration of treatment of 4 months for adalimumab-treated subjects and 4 months for control-treated subjects). In 52 global controlled and uncontrolled clinical trials of adalimumab in adult patients with RA, PsA, AS, CD, UC, Ps, HS and UV, the most frequently observed malignancies, other than lymphoma and NMSC, were breast, colon, prostate, lung, and melanoma. The malignancies in adalimumab-treated subjects in the controlled and uncontrolled portions of the studies were similar in type and number to what would be expected in the general U.S. population according to the SEER database (adjusted for age, gender, and race).^1

In controlled trials of other TNF blockers in adult patients at higher risk for malignancies (i.e., subjects with COPD with a significant smoking history and cyclophosphamide-treated patients with Wegener’s granulomatosis), a greater portion of malignancies occurred in the TNF blocker group compared to the control group.

Non-Melanoma Skin Cancer

During the controlled portions of 39 global adalimumab clinical trials in adult patients with RA, PsA, AS, CD, UC, Ps, HS and UV, the rate (95% confidence interval) of NMSC was 0.8 (0.52, 1.09) per 100 patient-years among adalimumab-treated subjects and 0.2 (0.10, 0.59) per 100 patient-years among control-treated subjects. Examine all patients, and in particular patients with a medical history of prior prolonged immunosuppressant therapy or psoriasis patients with a history of PUVA treatment for the presence of NMSC prior to and during treatment with Adalimumab-adaz.

Lymphoma and Leukemia

In the controlled portions of clinical trials of all the TNF-blockers in adults, more cases of lymphoma have been observed among TNF-blocker-treated subjects compared to control-treated subjects. In the controlled portions of 39 global adalimumab clinical trials in adult patients with RA, PsA, AS, CD, UC, Ps, HS and UV, 2 lymphomas occurred among 7973 adalimumab-treated subjects versus 1 among 4848 control-treated subjects. In 52 global controlled and uncontrolled clinical trials of adalimumab in adult patients with RA, PsA, AS, CD, UC, Ps, HS and UV with a median duration of approximately 0.7 years, including 24,605 subjects and over 40,215 patient-years of adalimumab, the observed rate of lymphomas was approximately 0.11 per 100 patient-years. This is approximately 3-fold higher than expected in the general U.S. population according to the SEER database (adjusted for age, gender, and race).^1 Rates of lymphoma in clinical trials of adalimumab cannot be compared to rates of lymphoma in clinical trials of other TNF blockers and may not predict the rates observed in a broader patient population. Patients with RA and other chronic inflammatory diseases, particularly those with highly active disease and/or chronic exposure to immunosuppressant therapies, may be at a higher risk (up to several fold) than the general population for the development of lymphoma, even in the absence of TNF blockers. Post-marketing cases of acute and chronic leukemia have been reported in association with TNF-blocker use in RA and other indications. Even in the absence of TNF-blocker therapy, patients with RA may be at a higher risk (approximately 2-fold) than the general population for the development of leukemia.

Malignancies in Pediatric Patients and Young Adults

Malignancies, some fatal, have been reported among children, adolescents, and young adults who received treatment with TNF-blockers (initiation of therapy ≤ 18 years of age), of which Adalimumab-adaz is a member. Approximately half the cases were lymphomas, including Hodgkin's and non-Hodgkin's lymphoma. The other cases represented a variety of different malignancies and included rare malignancies usually associated with immunosuppression and malignancies that are not usually observed in children and adolescents. The malignancies occurred after a median of 30 months of therapy (range 1 to 84 months). Most of the patients were receiving concomitant immunosuppressants. These cases were reported post-marketing and are derived from a variety of sources including registries and spontaneous postmarketing reports.

Postmarketing cases of hepatosplenic T-cell lymphoma (HSTCL), a rare type of T-cell lymphoma, have been reported in patients treated with TNF blockers including adalimumab products. These cases have had a very aggressive disease course and have been fatal. The majority of reported TNF blocker cases have occurred in patients with Crohn's disease or ulcerative colitis and the majority were in adolescent and young adult males. Almost all of these patients had received treatment with the immunosuppressants azathioprine or 6-mercaptopurine (6–MP) concomitantly with a TNF blocker at or prior to diagnosis. It is uncertain whether the occurrence of HSTCL is related to use of a TNF blocker or a TNF blocker in combination with these other immunosuppressants. The potential risk with the combination of azathioprine or 6-mercaptopurine and Adalimumab-adaz should be carefully considered.

5.3 Hypersensitivity Reactions

Anaphylaxis and angioneurotic edema have been reported following administration of adalimumab products. If an anaphylactic or other serious allergic reaction occurs, immediately discontinue administration of Adalimumab-adaz and institute appropriate therapy. In clinical trials of adalimumab, hypersensitivity reactions (e.g., rash, anaphylactoid reaction, fixed drug reaction, non-specified drug reaction, urticaria) have been observed.

5.4 Hepatitis B Virus Reactivation

Use of TNF blockers, including Adalimumab-adaz, may increase the risk of reactivation of hepatitis B virus (HBV) in patients who are chronic carriers of this virus. In some instances, HBV reactivation occurring in conjunction with TNF blocker therapy has been fatal. The majority of these reports have occurred in patients concomitantly receiving other medications that suppress the immune system, which may also contribute to HBV reactivation. Evaluate patients at risk for HBV infection for prior evidence of HBV infection before initiating TNF blocker therapy. Exercise caution in prescribing TNF blockers for patients identified as carriers of HBV. Adequate data are not available on the safety or efficacy of treating patients who are carriers of HBV with anti-viral therapy in conjunction with TNF blocker therapy to prevent HBV reactivation. For patients who are carriers of HBV and require treatment with TNF blockers, closely monitor such patients for clinical and laboratory signs of active HBV infection throughout therapy and for several months following termination of therapy. In patients who develop HBV reactivation, stop Adalimumab-adaz and initiate effective anti-viral therapy with appropriate supportive treatment. The safety of resuming TNF blocker therapy after HBV reactivation is controlled is not known. Therefore, exercise caution when considering resumption of Adalimumab-adaz therapy in this situation and monitor patients closely.

5.5 Neurologic Reactions

Use of TNF blocking agents, including adalimumab products, has been associated with rare cases of new onset or exacerbation of clinical symptoms and/or radiographic evidence of central nervous system demyelinating disease, including multiple sclerosis (MS) and optic neuritis, and peripheral demyelinating disease, including Guillain-Barré syndrome. Exercise caution in considering the use of Adalimumab-adaz in patients with preexisting or recent-onset central or peripheral nervous system demyelinating disorders; discontinuation of Adalimumab-adaz should be considered if any of these disorders develop. There is a known association between intermediate uveitis and central demyelinating disorders.

5.6 Hematological Reactions

Rare reports of pancytopenia including aplastic anemia have been reported with TNF blocking agents. Adverse reactions of the hematologic system, including medically significant cytopenia (e.g., thrombocytopenia, leukopenia) have been infrequently reported with adalimumab products. The causal relationship of these reports to adalimumab products remains unclear. Advise all patients to seek immediate medical attention if they develop signs and symptoms suggestive of blood dyscrasias or infection (e.g., persistent fever, bruising, bleeding, pallor) while on Adalimumab-adaz. Consider discontinuation of Adalimumab-adaz therapy in patients with confirmed significant hematologic abnormalities.

5.7 Increased Risk of Infection When Used with Anakinra

Concurrent use of anakinra (an interleukin-1 antagonist) and another TNF-blocker, was associated with a greater proportion of serious infections and neutropenia and no added benefit compared with the TNF-blocker alone in patients with RA. Therefore, the combination of Adalimumab-adaz and anakinra is not recommended [see Drug Interactions (7.2)].

5.8 Heart Failure

Cases of worsening congestive heart failure (CHF) and new onset CHF have been reported with TNF blockers. Cases of worsening CHF have also been observed with adalimumab products. Adalimumab products have not been formally studied in patients with CHF; however, in clinical trials of another TNF blocker, a higher rate of serious CHF-related adverse reactions was observed. Exercise caution when using Adalimumab-adaz in patients who have heart failure and monitor them carefully.

5.9 Autoimmunity

Treatment with adalimumab products may result in the formation of autoantibodies and, rarely, in the development of a lupus-like syndrome or autoimmune hepatitis [see Adverse Reactions (6.1, 6.3)]. If a patient develops symptoms and findings suggestive of a lupus-like syndrome or autoimmune hepatitis following treatment with Adalimumab-adaz, discontinue treatment and evaluate the patient.

5.10 Immunizations

In a placebo-controlled clinical trial of patients with RA, no difference was detected in anti-pneumococcal antibody response between adalimumab and placebo treatment groups when the pneumococcal polysaccharide vaccine and influenza vaccine were administered concurrently with adalimumab. Similar proportions of subjects developed protective levels of anti-influenza antibodies between adalimumab and placebo treatment groups; however, titers in aggregate to influenza antigens were moderately lower in patients receiving adalimumab. The clinical significance of this is unknown. Patients on Adalimumab-adaz may receive concurrent vaccinations, except for live vaccines. No data are available on the secondary transmission of infection by live vaccines in patients receiving adalimumab products.

It is recommended that pediatric patients, if possible, be brought up to date with all immunizations in agreement with current immunization guidelines prior to initiating Adalimumab-adaz therapy. Patients on Adalimumab-adaz may receive concurrent vaccinations, except for live vaccines.

The safety of administering live or live-attenuated vaccines in infants exposed to adalimumab products in utero is unknown. Risks and benefits should be considered prior to vaccinating (live or live-attenuated) exposed infants [see Use in Specific Populations (8.1, 8.4)].

5.11 Increased Risk of Infection When Used with Abatacept

In controlled trials, the concurrent administration of TNF-blockers and abatacept was associated with a greater proportion of serious infections than the use of a TNF-blocker alone; the combination therapy, compared to the use of a TNF-blocker alone, has not demonstrated improved clinical benefit in the treatment of RA. Therefore, the combination of abatacept with TNF-blockers including Adalimumab-adaz is not recommended [see Drug Interactions (7.2)].

6 ADVERSE REACTIONS

The following clinically significant adverse reactions are described elsewhere in the labeling:

- Serious Infections [see Warnings and Precautions (5.1)]
- Malignancies [see Warnings and Precautions (5.2)]
- Hypersensitivity Reactions [see Warnings and Precautions (5.3)]
- Hepatitis B Virus Reactivation [see Warnings and Precautions (5.4)]
- Neurologic Reactions [see Warnings and Precautions (5.5)]
- Hematological Reactions [see Warnings and Precautions (5.6)]
- Heart Failure [see Warnings and Precautions (5.8)]
- Autoimmunity [see Warnings and Precautions (5.9)]

6.1 Clinical Trials Experience

Because clinical trials are conducted under widely varying conditions, adverse reaction rates observed in the clinical trials of a drug cannot be directly compared to rates in the clinical trials of another drug and may not reflect the rates observed in practice.

The most common adverse reaction with adalimumab was injection site reactions. In placebo-controlled trials, 20% of subjects treated with adalimumab developed injection site reactions (erythema and/or itching, hemorrhage, pain or swelling), compared to 14% of subjects receiving placebo. Most injection site reactions were described as mild and generally did not necessitate drug discontinuation.

The proportion of subjects who discontinued treatment due to adverse reactions during the double-blind, placebo-controlled portion of studies in subjects with RA (i.e., Studies RA-I, RA-II, RA-III and RA-IV) was 7% for subjects taking adalimumab and 4% for placebo-treated subjects. The most common adverse reactions leading to discontinuation of adalimumab in these RA studies were clinical flare reaction (0.7%), rash (0.3%) and pneumonia (0.3%).

Infections

In the controlled portions of the 39 global adalimumab clinical trials in adult subjects with RA, PsA, AS, CD, UC, Ps, HS and UV, the rate of serious infections was 4.3 per 100 patient-years in 7973 adalimumab-treated subjects versus a rate of 2.9 per 100 patient-years in 4848 control-treated subjects. Serious infections observed included pneumonia, septic arthritis, prosthetic and post-surgical infections, erysipelas, cellulitis, diverticulitis, and pyelonephritis [see Warnings and Precautions (5.1)].

Tuberculosis and Opportunistic Infections

In 52 global controlled and uncontrolled clinical trials in RA, PsA, AS, CD, UC, Ps, HS and UV that included 24,605 adalimumab treated subjects, the rate of reported active tuberculosis was 0.20 per 100 patient-years and the rate of positive PPD conversion was 0.09 per 100 patient-years. In a subgroup of 10,113 U.S. and Canadian adalimumab treated subjects, the rate of reported active TB was 0.05 per 100 patient-years and the rate of positive PPD conversion was 0.07 per 100 patient-years. These trials included reports of miliary, lymphatic, peritoneal, and pulmonary TB. Most of the TB cases occurred within the first eight months after initiation of therapy and may reflect recrudescence of latent disease. In these global clinical trials, cases of serious opportunistic infections have been reported at an overall rate of 0.05 per 100 patient-years. Some cases of serious opportunistic infections and TB have been fatal [see Warnings and Precautions (5.1)].

Autoantibodies

In the rheumatoid arthritis controlled trials, 12% of subjects treated with adalimumab and 7% of placebo-treated subjects that had negative baseline ANA titers developed positive titers at Week 24. Two subjects out of 3046 treated with adalimumab developed clinical signs suggestive of new-onset lupus-like syndrome. The subjects improved following discontinuation of therapy. No subjects developed lupus nephritis or central nervous system symptoms. The impact of long-term treatment with adalimumab products on the development of autoimmune diseases is unknown.

Liver Enzyme Elevations

There have been reports of severe hepatic reactions including acute liver failure in subjects receiving TNF-blockers. In controlled Phase 3 trials of adalimumab (40 mg SC every other week) in subjects with RA, PsA, and AS with control period duration ranging from 4 to 104 weeks, ALT elevations ≥ 3 x ULN occurred in 3.5% of adalimumab-treated subjects and 1.5% of control-treated subjects. Since many of these subjects in these trials were also taking medications that cause liver enzyme elevations (e.g., NSAIDs, MTX), the relationship between adalimumab and the liver enzyme elevations is not clear. In a controlled Phase 3 trial of adalimumab in subjects with polyarticular JIA who were 4 to 17 years, ALT elevations ≥ 3 x ULN occurred in 4.4% of adalimumab-treated subjects and 1.5% of control-treated subjects (ALT more common than AST); liver enzyme test elevations were more frequent among those treated with the combination of adalimumab and MTX than those treated with adalimumab alone. In general, these elevations did not lead to discontinuation of adalimumab treatment. No ALT elevations ≥ 3 x ULN occurred in the open-label study of adalimumab in subjects with polyarticular JIA who were 2 to <4 years.

In controlled Phase 3 trials of adalimumab (initial doses of 160 mg and 80 mg, or 80 mg and 40 mg on Days 1 and 15, respectively, followed by 40 mg every other week) in adult subjects with Crohn’s Disease with a control period duration ranging from 4 to 52 weeks, ALT elevations ≥ 3 x ULN occurred in 0.9% of adalimumab-treated subjects and 0.9% of control-treated subjects. In the Phase 3 trial of adalimumab in pediatric subjects with Crohn’s disease which evaluated efficacy and safety of two body weight based maintenance dose regimens following body weight based induction therapy up to 52 weeks of treatment, ALT elevations ≥ 3 x ULN occurred in 2.6% (5/192) of subjects, of whom 4 were receiving concomitant immunosuppressants at baseline; none of these subjects discontinued due to abnormalities in ALT tests.

In controlled Phase 3 trials of adalimumab (initial doses of 160 mg and 80 mg on Days 1 and 15 respectively, followed by 40 mg every other week) in adult subjects with UC with control period duration ranging from 1 to 52 weeks, ALT elevations ≥3 x ULN occurred in 1.5% of adalimumab-treated subjects and 1.0% of control-treated subjects. In controlled Phase 3 trials of adalimumab (initial dose of 80 mg then 40 mg every other week) in subjects with Ps with control period duration ranging from 12 to 24 weeks, ALT elevations ≥ 3 x ULN occurred in 1.8% of adalimumab-treated subjects and 1.8% of control-treated subjects.

In controlled trials of adalimumab (initial doses of 160 mg at Week 0 and 80 mg at Week 2, followed by 40 mg every week starting at Week 4), in subjects with HS with a control period duration ranging from 12 to 16 weeks, ALT elevations ≥ 3 x ULN occurred in 0.3% of adalimumab-treated subjects and 0.6% of control-treated subjects.

In controlled trials of adalimumab (initial doses of 80 mg at Week 0 followed by 40 mg every other week starting at Week 1) in adult subjects with uveitis with an exposure of 165.4 PYs and 119.8 PYs in adalimumab-treated and control-treated subjects, respectively, ALT elevations ≥ 3 x ULN occurred in 2.4% of adalimumab-treated subjects and 2.4% of control-treated subjects.

Other Adverse Reactions

Rheumatoid Arthritis Clinical Studies

The data described below reflect exposure to adalimumab in 2468 subjects, including 2073 exposed for 6 months, 1497 exposed for greater than one year and 1380 in adequate and well-controlled studies (Studies RA-I, RA-II, RA-III, and RA-IV). Adalimumab was studied primarily in placebo-controlled trials and in long-term follow up studies for up to 36 months duration. The population had a mean age of 54 years, 77% were female, 91% were Caucasian and had moderately to severely active rheumatoid arthritis. Most subjects received 40 mg adalimumab every other week [see Clinical Studies (14.1)].

Table 1 summarizes reactions reported at a rate of at least 5% in subjects treated with adalimumab 40 mg every other week compared to placebo and with an incidence higher than placebo. In Study RA-III, the types and frequencies of adverse reactions in the second year open-label extension were similar to those observed in the one-year double-blind portion.

Table 1. Adverse Reactions Reported by ≥5% of Subjects Treated with Adalimumab During Placebo-Controlled Period of Pooled RA Studies (Studies RA-I, RA-II, RA-III, and RA-IV)

 | Adalimumab; 40 mg subcutaneous; Every Other Week | Placebo
 | (N=705) | (N=690)
Adverse Reaction (Preferred Term)
Respiratory
Upper respiratory infection | 17 % | 13 %
Sinusitis | 11 % | 9 %
Flu syndrome | 7 % | 6 %
Gastrointestinal
Nausea | 9 % | 8 %
Abdominal pain | 7 % | 4 %
Laboratory Tests*
Laboratory test abnormal | 8 % | 7 %
Hypercholesterolemia | 6 % | 4 %
Hyperlipidemia | 7 % | 5 %
Hematuria | 5 % | 4 %
Alkaline phosphatase increased | 5 % | 3 %
Other
Headache | 12 % | 8 %
Rash | 12 % | 6 %
Accidental injury | 10 % | 8 %
Injection site reaction ** | 8 % | 1 %
Back pain | 6 % | 4 %
Urinary tract infection | 8 % | 5 %
Hypertension | 5 % | 3 %
* Laboratory test abnormalities were reported as adverse reactions in European trials.
** Does not include injection site erythema, itching, hemorrhage, pain or swelling.

Less Common Adverse Reactions in Rheumatoid Arthritis Clinical Studies

Other infrequent serious adverse reactions that do not appear in the Warnings and Precautions or Adverse Reaction sections that occurred at an incidence of less than 5% in adalimumab-treated subjects in RA studies (RA-I, RA-II, RA-III, and RA-IV) were:

Body As A Whole: Pain in extremity, pelvic pain, surgery, thorax pain

Cardiovascular System: Arrhythmia, atrial fibrillation, chest pain, coronary artery disorder, heart arrest, hypertensive encephalopathy, myocardial infarct, palpitation, pericardial effusion, pericarditis, syncope, tachycardia

Digestive System: Cholecystitis, cholelithiasis, esophagitis, gastroenteritis, gastrointestinal hemorrhage, hepatic necrosis, vomiting

Endocrine System: Parathyroid disorder

Hemic And Lymphatic System: Agranulocytosis, polycythemia

Metabolic And Nutritional Disorders: Dehydration, healing abnormal, ketosis, paraproteinemia, peripheral edema

Musculo-Skeletal System: Arthritis, bone disorder, bone fracture (not spontaneous), bone necrosis, joint disorder, muscle cramps, myasthenia, pyogenic arthritis, synovitis, tendon disorder

Neoplasia: Adenoma

Nervous System: Confusion, paresthesia, subdural hematoma, tremor

Respiratory System: Asthma, bronchospasm, dyspnea, lung function decreased, pleural effusion

Special Senses: Cataract

Thrombosis: Thrombosis leg

Urogenital System: Cystitis, kidney calculus, menstrual disorder

Juvenile Idiopathic Arthritis Clinical Studies

In general, the adverse reactions in the adalimumab-treated subjects in the polyarticular juvenile idiopathic arthritis (JIA) trials (Studies JIA-I and JIA-II) [see Clinical Studies (14.2)] were similar in frequency and type to those seen in adult subjects [see Warnings and Precautions (5), Adverse Reactions (6)]. Important findings and differences from adults are discussed in the following paragraphs.

In Study JIA-I, adalimumab was studied in 171 subjects who were 4 to 17 years of age, with polyarticular JIA. Severe adverse reactions reported in the study included neutropenia, streptococcal pharyngitis, increased aminotransferases, herpes zoster, myositis, metrorrhagia, and appendicitis. Serious infections were observed in 4% of subjects within approximately 2 years of initiation of treatment with adalimumab and included cases of herpes simplex, pneumonia, urinary tract infection, pharyngitis, and herpes zoster.

In Study JIA-I, 45% of subjects experienced an infection while receiving adalimumab with or without concomitant MTX in the first 16 weeks of treatment. The types of infections reported in adalimumab-treated subjects were generally similar to those commonly seen in polyarticular JIA subjects who are not treated with TNF blockers. Upon initiation of treatment, the most common adverse reactions occurring in this population treated with adalimumab were injection site pain and injection site reaction (19% and 16%, respectively). A less commonly reported adverse event in subjects receiving adalimumab was granuloma annulare which did not lead to discontinuation of adalimumab treatment.

In the first 48 weeks of treatment in Study JIA-I, non-serious hypersensitivity reactions were seen in approximately 6% of subjects and included primarily localized allergic hypersensitivity reactions and allergic rash.

In Study JIA-I, 10% of subjects treated with adalimumab who had negative baseline anti-dsDNA antibodies developed positive titers after 48 weeks of treatment. No subject developed clinical signs of autoimmunity during the clinical trial.

Approximately 15% of subjects treated with adalimumab developed mild-to-moderate elevations of creatine phosphokinase (CPK) in Study JIA-I. Elevations exceeding 5 times the upper limit of normal were observed in several subjects. CPK concentrations decreased or returned to normal in all subjects. Most subjects were able to continue adalimumab without interruption.

In Study JIA-II, adalimumab was studied in 32 subjects who were 2 to <4 years of age or 4 years of age and older weighing <15 kg with polyarticular JIA. The safety profile for this population was similar to the safety profile seen in subjects 4 to 17 years of age with polyarticular JIA.

In Study JIA-II, 78% of subjects experienced an infection while receiving adalimumab. These included nasopharyngitis, bronchitis, upper respiratory tract infection, otitis media, and were mostly mild to moderate in severity. Serious infections were observed in 9% of subjects receiving adalimumab in the study and included dental caries, rotavirus gastroenteritis, and varicella.

In Study JIA-II, non-serious allergic reactions were observed in 6% of subjects and included intermittent urticaria and rash, which were all mild in severity.

Psoriatic Arthritis and Ankylosing Spondylitis Clinical Studies

Adalimumab has been studied in 395 subjects with psoriatic arthritis (PsA) in two placebo-controlled trials and in an open label study and in 393 subjects with ankylosing spondylitis (AS) in two placebo-controlled studies [see Clinical Studies (14.3, 14.4)]. The safety profile for subjects with PsA and AS treated with adalimumab 40 mg every other week was similar to the safety profile seen in subjects with RA, adalimumab Studies RA-I through IV.

Crohn’s Disease Clinical Studies

Adults: The safety profile of adalimumab in 1478 adult subjects with Crohn’s disease from four placebo-controlled and two open-label extension studies [see Clinical Studies (14.5)] was similar to the safety profile seen in subjects with RA.

Pediatric Patients 6 Years to 17 Years: The safety profile of adalimumab in 192 pediatric subjects from one double-blind study (Study PCD-I) and one open-label extension study [see Clinical Studies (14.6)] was similar to the safety profile seen in adult subjects with Crohn’s disease.

During the 4-week open label induction phase of Study PCD-I, the most common adverse reactions occurring in the pediatric population treated with adalimumab were injection site pain and injection site reaction (6% and 5%, respectively).

A total of 67% of children experienced an infection while receiving adalimumab in Study PCD-I. These included upper respiratory tract infection and nasopharyngitis.

A total of 5% of children experienced a serious infection while receiving adalimumab in Study PCD-I. These included viral infection, device related sepsis (catheter), gastroenteritis, H1N1 influenza, and disseminated histoplasmosis.

In Study PCD-I, allergic reactions were observed in 5% of children which were all non-serious and were primarily localized reactions.

Ulcerative Colitis Clinical Studies

Adults: The safety profile of adalimumab in 1010 adult subjects with ulcerative colitis (UC) from two placebo-controlled studies and one open-label extension study [see Clinical Studies (14.7)] was similar to the safety profile seen in subjects with RA.

Plaque Psoriasis Clinical Studies

Adalimumab has been studied in 1696 subjects with plaque psoriasis (Ps) in placebo-controlled and open-label extension studies [see Clinical Studies (14.9)]. The safety profile for subjects with Ps treated with adalimumab was similar to the safety profile seen in subjects with RA with the following exceptions. In the placebo-controlled portions of the clinical trials in Ps subjects, adalimumab-treated subjects had a higher incidence of arthralgia when compared to controls (3% vs. 1%).

Hidradenitis Suppurativa Clinical Studies

Adalimumab has been studied in 727 subjects with hidradenitis suppurativa (HS) in three placebo-controlled studies and one open-label extension study [see Clinical Studies (14.10)]. The safety profile for subjects with HS treated with adalimumab weekly was consistent with the known safety profile of adalimumab.

Flare of HS, defined as ≥25% increase from baseline in abscesses and inflammatory nodule counts and with a minimum of 2 additional lesions, was documented in 22 (22%) of the 100 subjects who were withdrawn from adalimumab treatment following the primary efficacy timepoint in two studies.

Uveitis Clinical Studies

Adalimumab has been studied in 464 adult subjects with uveitis (UV) in placebo-controlled and open-label extension studies and in 90 pediatric subjects with uveitis (Study PUV-I) [see Clinical Studies (14.11, 14.12)] . The safety profile for subjects with UV treated with adalimumab was similar to the safety profile seen in subjects with RA.

6.2 Immunogenicity

The observed incidence of anti-drug antibodies is highly dependent on the sensitivity and specificity of the assay. Differences in assay methods preclude meaningful comparisons of the incidence of anti-drug antibodies in the studies described below with the incidence of anti-drug antibodies in other studies, including those of adalimumab or of other adalimumab products.

There are two assays that have been used to measure anti-adalimumab antibodies. With the ELISA, antibodies to adalimumab could be detected only when serum adalimumab concentrations were < 2 mcg/mL. The ECL assay can detect anti-adalimumab antibody titers independent of adalimumab concentrations in the serum samples. The incidence of anti-adalimumab antibody (AAA) development in patients treated with adalimumab are presented in Table 2.

Table 2. Anti-Adalimumab Antibody Development Determined by ELISA and ECL Assay in Patients Treated with adalimumab

Indications |  | Study Duration | Anti-Adalimumab Antibody Incidence by ELISA (n/N) |  | Anti-Adalimumab Antibody Incidence by ECL Assay (n/N)
Indications |  | Study Duration | In all patients who received adalimumab | In patients with serum adalimumab concentrations < 2 mcg/mL
Rheumatoid Arthritis [In patients receiving concomitant methotrexate (MTX), the incidence of anti-adalimumab antibody was 1% compared to 12% with adalimumab monotherapy.] |  | 6 to 12 months | 5% (58/1062) | NR | NA
Juvenile Idiopathic Arthritis (JIA) | 4 to 17 years of age [In patients receiving concomitant MTX, the incidence of anti-adalimumab antibody was 6% compared to 26% with adalimumab monotherapy.] | 48 weeks | 16% (27/171) | NR | NA
Juvenile Idiopathic Arthritis (JIA) | 2 to 4 years of age or ≥ 4 years of age and weighing < 15 kg | 24 weeks | 7% (1/15) [This patient received concomitant MTX.] | NR | NA
Psoriatic Arthritis [In patients receiving concomitant MTX, the incidence of antibody development was 7% compared to 1% in RA.] |  | 48 weeks [Subjects enrolled after completing 2 previous studies of 24 weeks or 12 weeks of treatments.] | 13% (24/178) | NR | NA
Ankylosing Spondylitis |  | 24 weeks | 9% (16/185) | NR | NA
Adult Crohn’s Disease |  | 56 weeks | 3% (7/269) | 8% (7/86) | NA
Pediatric Crohn’s Disease |  | 52 weeks | 3% (6/182) | 10% (6/58) | NA
Adult Ulcerative Colitis |  | 52 weeks | 5% (19/360) | 21% (19/92) | NA
Plaque Psoriasis [In plaque psoriasis patients who were on adalimumab monotherapy and subsequently withdrawn from the treatment, the rate of antibodies to adalimumab after retreatment was similar to the rate observed prior to withdrawal.] |  | Up to 52 weeks [One 12-week Phase 2 study and one 52-week Phase 3 study.] | 8% (77/920) | 21% (77/372) | NA
Hidradenitis Suppurativa |  | 36 weeks | 7% (30/461) | 28% (58/207) [Among subjects in the 2 Phase 3 studies who stopped adalimumab treatment for up to 24 weeks and in whom adalimumab serum levels subsequently declined to <2 mcg/mL (approximately 22% of total subjects studied).] | 61% (272/445) [No apparent association between antibody development and safety was observed.]
Non-infectious Uveitis |  | 52 weeks | 5% (12/249) | 21% (12/57) | 40% (99/249) [No correlation of antibody development to safety or efficacy outcomes was observed.]
n: number of patients with anti-adalimumab antibody; NR: not reported; NA: Not applicable (not performed).

Rheumatoid Arthritis and Psoriatic Arthritis: Subjects in Studies RA-I, RA-II, and RA-III were tested at multiple time points for antibodies to adalimumab using the ELISA during the 6 to 12 month period. No apparent correlation of antibody development to adverse reactions was observed. With monotherapy, subjects receiving every other week dosing may develop antibodies more frequently than those receiving weekly dosing. In subjects receiving the recommended dosage of 40 mg every other week as monotherapy, the ACR 20 response was lower among antibody-positive subjects than among antibody-negative subjects. The long-term immunogenicity of adalimumab products is unknown.

6.3 Postmarketing Experience

The following adverse reactions have been identified during post-approval use of adalimumab products. Because these reactions are reported voluntarily from a population of uncertain size, it is not always possible to reliably estimate their frequency or establish a causal relationship to adalimumab products exposure.

Gastrointestinal disorders: Diverticulitis, large bowel perforations including perforations associated with diverticulitis and appendiceal perforations associated with appendicitis, pancreatitis

General disorders and administration site conditions: Pyrexia

Hepato-biliary disorders: Liver failure, hepatitis, autoimmune hepatitis

Immune system disorders: Sarcoidosis

Neoplasms benign, malignant and unspecified (including cysts and polyps): Merkel Cell Carcinoma (neuroendocrine carcinoma of the skin)

Nervous system disorders: Demyelinating disorders (e.g., optic neuritis, Guillain-Barré syndrome), cerebrovascular accident

Respiratory disorders: Interstitial lung disease, including pulmonary fibrosis, pulmonary embolism

Skin reactions: Stevens Johnson Syndrome, cutaneous vasculitis, erythema multiforme, new or worsening psoriasis (all sub-types including pustular and palmoplantar), alopecia, lichenoid skin reaction

Vascular disorders: Systemic vasculitis, deep vein thrombosis

7 DRUG INTERACTIONS

7.1 Methotrexate

Adalimumab has been studied in rheumatoid arthritis (RA) patients taking concomitant methotrexate (MTX). Although MTX reduced the apparent clearance of adalimumab, the data do not suggest the need for dose adjustment of either Adalimumab-adaz or MTX [see Clinical Pharmacology (12.3)].

7.2 Biological Products

In clinical studies in patients with RA, an increased risk of serious infections has been observed with the combination of TNF-blockers with anakinra or abatacept, with no added benefit; therefore, use of Adalimumab-adaz with abatacept or anakinra is not recommended in patients with RA [see Warnings and Precautions (5.7, 5.11)]. A higher rate of serious infections has also been observed in patients with RA treated with rituximab who received subsequent treatment with a TNF-blocker. There is insufficient information regarding the concomitant use of Adalimumab-adaz and other biologic products for the treatment of RA, PsA, AS, CD, UC, Ps, HS and UV. Concomitant administration of Adalimumab-adaz with other biologic DMARDs (e.g., anakinra and abatacept) or other TNF-blockers is not recommended based upon the possible increased risk for infections and other potential pharmacological interactions.

7.3 Live Vaccines

Avoid the use of live vaccines with Adalimumab-adaz [see Warnings and Precautions (5.10)].

7.4 Cytochrome P450 Substrates

The formation of CYP450 enzymes may be suppressed by increased concentrations of cytokines (e.g., TNFα, IL-6) during chronic inflammation. It is possible for products that antagonize cytokine activity, such as adalimumab products, to influence the formation of CYP450 enzymes. Upon initiation or discontinuation of Adalimumab-adaz in patients being treated with CYP450 substrates with a narrow therapeutic index, monitoring of the effect (e.g., warfarin) or drug concentration (e.g., cyclosporine or theophylline) is recommended and the individual dose of the drug product may be adjusted as needed.

8 USE IN SPECIFIC POPULATIONS

8.1 Pregnancy

Risk Summary

Available studies with use of adalimumab during pregnancy do not reliably establish an association between adalimumab and major birth defects. Clinical data are available from the Organization of Teratology Information Specialists (OTIS)/MotherToBaby Pregnancy Registry in pregnant women with rheumatoid arthritis (RA) or Crohn’s disease (CD) treated with adalimumab. Registry results showed a rate of 10% for major birth defects with first trimester use of adalimumab in pregnant women with RA or CD and a rate of 7.5% for major birth defects in the disease-matched comparison cohort. The lack of pattern of major birth defects is reassuring and differences between exposure groups may have impacted the occurrence of birth defects (see Data).

Adalimumab is actively transferred across the placenta during the third trimester of pregnancy and may affect immune response in the in-utero exposed infant (see Clinical Considerations). In an embryo-fetal perinatal development study conducted in cynomolgus monkeys, no fetal harm or malformations were observed with intravenous administration of adalimumab during organogenesis and later in gestation, at doses that produced exposures up to approximately 373 times the maximum recommended human dose (MRHD) of 40 mg subcutaneous without methotrexate (see Data).

The estimated background risk of major birth defects and miscarriage for the indicated populations is unknown. All pregnancies have a background risk of birth defect, loss, or other adverse outcomes. In the U.S. general population, the estimated background risk of major birth defects and miscarriage in clinically recognized pregnancies is 2-4% and 15-20%, respectively.

Clinical Considerations

Disease-associated maternal and embryo/fetal risk

Published data suggest that the risk of adverse pregnancy outcomes in women with RA or inflammatory bowel disease (IBD) is associated with increased disease activity. Adverse pregnancy outcomes include preterm delivery (before 37 weeks of gestation), low birth weight (less than 2500 g) infants, and small for gestational age at birth.

Fetal/Neonatal Adverse Reactions

Monoclonal antibodies are increasingly transported across the placenta as pregnancy progresses, with the largest amount transferred during the third trimester (see Data). Risks and benefits should be considered prior to administering live or live-attenuated vaccines to infants exposed to adalimumab products in utero [see Use in Specific Populations (8.4)].

Data

Human Data

A prospective cohort pregnancy exposure registry conducted by OTIS/MotherToBaby in the U.S. and Canada between 2004 and 2016 compared the risk of major birth defects in live-born infants of 221 women (69 RA, 152 CD) treated with adalimumab during the first trimester and 106 women (74 RA, 32 CD) not treated with adalimumab.

The proportion of major birth defects among live-born infants in the adalimumab-treated and untreated cohorts was 10% (8.7% RA, 10.5% CD) and 7.5% (6.8% RA, 9.4% CD), respectively. The lack of pattern of major birth defects is reassuring and differences between exposure groups may have impacted the occurrence of birth defects. This study cannot reliably establish whether there is an association between adalimumab and major birth defects because of methodological limitations of the registry, including small sample size, the voluntary nature of the study, and the non-randomized design.

In an independent clinical study conducted in ten pregnant women with IBD treated with adalimumab, adalimumab concentrations were measured in maternal serum as well as in cord blood (n=10) and infant serum (n=8) on the day of birth. The last dose of adalimumab was given between 1 and 56 days prior to delivery. Adalimumab concentrations were 0.16 to 19.7 mcg/mL in cord blood, 4.28 to 17.7 mcg/mL in infant serum, and 0 to 16.1 mcg/mL in maternal serum. In all but one case, the cord blood concentration of adalimumab was higher than the maternal serum concentration, suggesting adalimumab actively crosses the placenta. In addition, one infant had serum concentrations at each of the following: 6 weeks (1.94 mcg/mL), 7 weeks (1.31 mcg/mL), 8 weeks (0.93 mcg/mL), and 11 weeks (0.53 mcg/mL), suggesting adalimumab can be detected in the serum of infants exposed in utero for at least 3 months from birth.

Animal Data

In an embryo-fetal perinatal development study, pregnant cynomolgus monkeys received adalimumab from gestation days 20 to 97 at doses that produced exposures up to 373 times that achieved with the MRHD without methotrexate (on an AUC basis with maternal IV doses up to 100 mg/kg/week). Adalimumab did not elicit harm to the fetuses or malformations.

8.2 Lactation

Risk Summary

Limited data from case reports in the published literature describe the presence of adalimumab in human milk at infant doses of 0.1% to 1% of the maternal serum concentration. Published data suggest that the systemic exposure to a breastfed infant is expected to be low because adalimumab is a large molecule and is degraded in the gastrointestinal tract. However, the effects of local exposure in the gastrointestinal tract are unknown. There are no reports of adverse effects of adalimumab products on the breastfed infant and no effects on milk production. The developmental and health benefits of breastfeeding should be considered along with the mother’s clinical need for Adalimumab-adaz and any potential adverse effects on the breastfed child from Adalimumab-adaz or from the underlying maternal condition.

8.4 Pediatric Use

The safety and effectiveness of Adalimumab-adaz have not been established in pediatric patients with psoriatic arthritis, ankylosing spondylitis, or plaque psoriasis.

The safety and effectiveness of Adalimumab-adaz have been established for:

- reducing signs and symptoms of moderately to severely active polyarticular JIA in pediatric patients 2 years of age and older.
- the treatment of moderately to severely active Crohn’s disease in pediatric patients 6 years of age and older.
- the treatment of moderate to severe hidradenitis suppurativa in patients 12 years of age and older.
- the treatment of non-infectious intermediate, posterior, and panuveitis in pediatric patients 2 years of age and older.

Due to their inhibition of TNFα, adalimumab products administered during pregnancy could affect immune response in the in utero-exposed newborn and infant. Data from eight infants exposed to adalimumab in utero suggest adalimumab crosses the placenta [see Use in Specific Populations (8.1)]. The clinical significance of elevated adalimumab concentrations in infants is unknown. The safety of administering live or live-attenuated vaccines in exposed infants is unknown. Risks and benefits should be considered prior to vaccinating (live or live-attenuated) exposed infants.

Post-marketing cases of lymphoma, including hepatosplenic T-cell lymphoma and other malignancies, some fatal, have been reported among children, adolescents, and young adults who received treatment with TNF-blockers including adalimumab products [see Warnings and Precautions (5.2)].

Juvenile Idiopathic Arthritis

The safety and effectiveness of Adalimumab-adaz for the treatment of moderately to severely active polyarticular JIA have been established in pediatric patients 2 years of age and older. Use for this indication is supported by evidence from an adequate and well-controlled study (Study JIA) of adalimumab in patients 4 to 17 years of age [see Clinical Studies (14.2)] and a safety study (Study JIA-II) of adalimumab in patients 2 to < 4 years of age where the safety profile was similar to patients 4 to 17 years of age [see Adverse Reactions (6.1)]. Adalimumab products have not been studied in patients with polyarticular JIA less than 2 years of age or in patients with a weight below 10 kg.

The safety of adalimumab in pediatric patients in the polyarticular JIA trials was generally similar to that observed in adults with certain exceptions [see Adverse Reactions (6.1)].

The safety and effectiveness of Adalimumab-adaz have not been established in pediatric patients with JIA less than 2 years of age.

Pediatric Crohn’s Disease

The safety and effectiveness of Adalimumab-adaz for the treatment of moderately to severely active Crohn’s disease have been established in pediatric patients 6 years of age and older. Use of Adalimumab-adaz for this indication is supported by evidence from adequate and well-controlled studies in adults with additional data from a randomized, double-blind, 52-week clinical study of two dose concentrations of adalimumab in 192 pediatric patients (6 years to 17 years of age) [see Adverse Reactions (6.1), Clinical Pharmacology (12.2, 12.3), Clinical Studies (14.6)]. The adverse reaction profile in patients 6 years to 17 years of age was similar to adults.

The safety and effectiveness of Adalimumab-adaz have not been established in pediatric patients with Crohn’s disease less than 6 years of age.

Pediatric Uveitis

The safety and effectiveness of Adalimumab-adaz for the treatment of non-infectious, intermediate, posterior, and panuveitis have been established in pediatric patients 2 years of age and older. Use of Adalimumab-adaz for this indication is supported by evidence from adequate and well-controlled studies of adalimumab in adults and a 2:1 randomized, controlled clinical study of adalimumab in 90 pediatric patients [see Clinical Studies (14.12)]. The safety and effectiveness of Adalimumab-adaz have not been established in pediatric patients with uveitis less than 2 years of age.

Hidradenitis Suppurativa

Use of Adalimumab-adaz in pediatric patients 12 years of age and older for the treatment of moderate to severe HS is supported by evidence from adequate and well-controlled studies of adalimumab in adult HS patients. Additional population pharmacokinetic modeling and simulation predicted that weight-based dosing of adalimumab in pediatric patients 12 years of age and older can provide generally similar exposure to adult HS patients. The course of HS is sufficiently similar in adult and adolescent patients to allow extrapolation of data from adult to adolescent patients. The recommended dosage in pediatric patients 12 years of age or older is based on body weight [see Dosage and Administration (2.7), Clinical Pharmacology (12.3), and Clinical Studies (14.10)].

The safety and effectiveness of Adalimumab-adaz have not been established in patients less than 12 years of age with HS.

8.5 Geriatric Use

In clinical studies of RA (Studies RA-I, RA-II, RA-III, and RA-IV), a total of 519 subjects 65 years of age and older, including 107 subjects 75 years of age and older, received adalimumab. No overall difference in effectiveness was observed between these subjects and younger adult subjects.

The frequency of serious infection and malignancy among adalimumab treated subjects 65 years of age and older was higher than for those less than 65 years of age. Consider the benefits and risks of Adalimumab-adaz in patients 65 years of age and older. In patients treated with Adalimumab-adaz, closely monitor for the development of infection or malignancy [see Warnings and Precautions (5.1, 5.2)].

10 OVERDOSAGE

Doses up to 10 mg/kg have been administered to patients in clinical trials without evidence of dose-limiting toxicities. In case of overdosage, it is recommended that the patient be monitored for any signs or symptoms of adverse reactions or effects and appropriate symptomatic treatment instituted immediately.

Consider contacting the Poison Help line (1-800-222-1222) or medical toxicologist for additional overdose management recommendations.

11 DESCRIPTION

Adalimumab-adaz is a tumor necrosis factor blocker. Adalimumab-adaz is a recombinant human IgG1 monoclonal antibody with human derived heavy and light chain variable regions and human IgG1:k constant regions. Adalimumab-adaz is produced by recombinant DNA technology in a Chinese hamster ovary cell expression system and is purified by a process that includes specific viral inactivation and removal steps. It consists of 1330 amino acids and has a molecular weight of approximately 148 kilodaltons.

Adalimumab-adaz injection is supplied as a sterile, preservative-free solution for subcutaneous administration. The drug product is supplied as either a single-dose, prefilled pen (Sensoready Pen), or as a single-dose, prefilled 1 mL glass syringe with needle guard and add-on finger flange or as a single-dose, prefilled 1 mL glass syringe. Enclosed within the Pen is a single-dose, 1 mL prefilled glass syringe. The solution of Adalimumab-adaz is clear, colorless or slightly yellowish, with a pH of about 5.2.

Each 80 mg/0.8 mL prefilled Sensoready Pen or prefilled syringe with BD UltraSafe PassiveTM Needle Guard delivers 0.8 mL (80 mg) of drug product. Each 0.8 mL of Adalimumab-adaz contains adalimumab-adaz (80 mg), adipic acid (1.75 mg), mannitol (33.6 mg), polysorbate 80 (0.32 mg), and Water for Injection, USP. Hydrochloric acid and sodium hydroxide are added as necessary to adjust pH.

Each 40 mg/0.4 mL prefilled Sensoready Pen or prefilled syringe with BD UltraSafe PassiveTM Needle Guard delivers 0.4 mL (40 mg) of drug product. Each 0.4 mL of Adalimumab-adaz contains adalimumab-adaz (40 mg), adipic acid (0.88 mg), mannitol (16.8 mg), polysorbate 80 (0.16 mg) and Water for Injection, USP. Hydrochloric acid and sodium hydroxide are added as necessary to adjust pH.

Each 20 mg/0.2 mL prefilled syringe delivers 0.2 mL (20 mg) of drug product. Each 0.2 mL of Adalimumab-adaz contains adalimumab-adaz (20 mg), adipic acid (0.44 mg), mannitol (8.4 mg), polysorbate 80 (0.08 mg) and Water for Injection, USP. Hydrochloric acid and sodium hydroxide are added as necessary to adjust pH.

Each 10 mg/0.1 mL prefilled syringe delivers 0.1 mL (10 mg) of drug product. Each 0.1 mL of Adalimumab-adaz contains adalimumab-adaz (10 mg), adipic acid (0.22 mg), mannitol (4.2 mg), polysorbate 80 (0.04 mg) and Water for Injection, USP. Hydrochloric acid and sodium hydroxide are added as necessary to adjust pH.

12 CLINICAL PHARMACOLOGY

12.1 Mechanism of Action

Adalimumab products bind specifically to TNF-alpha and block its interaction with the p55 and p75 cell surface TNF receptors. Adalimumab products also lyse surface TNF expressing cells in vitro in the presence of complement. Adalimumab products do not bind or inactivate lymphotoxin (TNF-beta). TNF is a naturally occurring cytokine that is involved in normal inflammatory and immune responses. Elevated concentrations of TNF are found in the synovial fluid of patients with RA, JIA, PsA, and AS and play an important role in both the pathologic inflammation and the joint destruction that are hallmarks of these diseases. Increased concentrations of TNF are also found in psoriasis plaques. In Ps, treatment with Adalimumab-adaz may reduce the epidermal thickness and infiltration of inflammatory cells. The relationship between these pharmacodynamic activities and the mechanism(s) by which adalimumab products exert their clinical effects is unknown.

Adalimumab products also modulate biological responses that are induced or regulated by TNF, including changes in the concentrations of adhesion molecules responsible for leukocyte migration (ELAM-1, VCAM-1, and ICAM-1 with an IC50 of 1-2 X 10^-10M).

12.2 Pharmacodynamics

After treatment with adalimumab, a decrease in concentrations of acute phase reactants of inflammation (Creactive protein [CRP] and erythrocyte sedimentation rate [ESR]) and serum cytokines (IL-6) was observed compared to baseline in patients with rheumatoid arthritis. A decrease in CRP concentrations was also observed in patients with Crohn’s disease, ulcerative colitis and hidradenitis suppurativa. Serum concentrations of matrix metalloproteinases (MMP-1 and MMP-3) that produce tissue remodeling responsible for cartilage destruction were also decreased after adalimumab administration.

12.3 Pharmacokinetics

The pharmacokinetics of adalimumab were linear over the dose range of 0.5 to 10 mg/kg following administration of a single intravenous dose (adalimumab products are not approved for intravenous use). Following 20 mg, 40 mg, and 80 mg every other week and every week subcutaneous administration, adalimumab mean serum trough concentrations at steady state increased approximately proportionally with dose in RA patients. The mean terminal half-life was approximately 2 weeks, ranging from 10 to 20 days across studies. Healthy subjects and patients with RA displayed similar adalimumab pharmacokinetics.

Adalimumab exposure in patients treated with 80 mg every other week is estimated to be comparable with that in patients treated with 40 mg every week.

Absorption

The average absolute bioavailability of adalimumab following a single 40 mg subcutaneous dose was 64%. The mean time to reach the maximum concentration was 5.5 days (131 ± 56 hours) and the maximum serum concentration was 4.7 ± 1.6 mcg/mL in healthy subjects following a single 40 mg subcutaneous administration of adalimumab.

Distribution

The distribution volume (Vss) ranged from 4.7 to 6.0 L following intravenous administration of doses ranging from 0.25 to 10 mg/kg in RA patients.

Elimination

The single dose pharmacokinetics of adalimumab in RA patients were determined in several studies with intravenous doses ranging from 0.25 to 10 mg/kg. The systemic clearance of adalimumab is approximately 12 mL/hr. In long-term studies with dosing more than two years, there was no evidence of changes in clearance over time in RA patients.

Patient Population

Rheumatoid Arthritis and Ankylosing Spondylitis: In patients receiving 40 mg adalimumab every other week, adalimumab mean steady-state trough concentrations were approximately 5 mcg/mL and 8 to 9 mcg/mL, without and with MTX concomitant treatment, respectively. Adalimumab concentrations in the synovial fluid from five rheumatoid arthritis patients ranged from 31 to 96% of those in serum. The pharmacokinetics of adalimumab in patients with AS were similar to those in patients with RA.

Psoriatic Arthritis: In patients receiving 40 mg every other week, adalimumab mean steady-state trough concentrations were 6 to 10 mcg/mL and 8.5 to 12 mcg/mL, without and with MTX concomitant treatment, respectively.

Plaque Psoriasis: Adalimumab mean steady-state trough concentration was approximately 5 to 6 mcg/mL during adalimumab 40 mg every other week treatment.

Adult Uveitis: Adalimumab mean steady concentration was approximately 8 to 10 mcg/mL during adalimumab 40 mg every other week treatment.

Adult Hidradenitis Suppurativa: Adalimumab trough concentrations were approximately 7 to 8 mcg/mL at Week 2 and Week 4, respectively, after receiving 160 mg on Week 0 followed by 80 mg on Week 2. Mean steady-state trough concentrations at Week 12 through Week 36 were approximately 7 to 11 mcg/mL during adalimumab 40 mg every week treatment.

Adult Crohn’s Disease: Adalimumab mean trough concentrations were approximately 12 mcg/mL at Week 2 and Week 4 after receiving 160 mg on Week 0 followed by 80 mg on Week 2. Mean steady-state trough concentrations were 7 mcg/mL at Week 24 and Week 56 during adalimumab 40 mg every other week treatment.

Adult Ulcerative Colitis: Adalimumab mean trough concentrations were approximately 12 mcg/mL at Week 2 and Week 4 after receiving 160 mg on Week 0 followed by 80 mg on Week 2. Mean steady-state trough concentrations were approximately 8 mcg/mL and 15 mcg/mL at Week 52 after receiving a dose of adalimumab 40 mg every other week and 40 mg every week, respectively.

Anti-Drug Antibody Effects on Pharmacokinetics

Rheumatoid Arthritis: A trend toward higher apparent clearance of adalimumab in the presence of anti-adalimumab antibodies was identified.

Hidradenitis Suppurativa: In subjects with moderate to severe HS, antibodies to adalimumab were associated with reduced serum adalimumab concentrations. In general, the extent of reduction in serum adalimumab concentrations is greater with increasing titers of antibodies to adalimumab.

Specific Populations

Geriatric Patients: A lower clearance with increasing age was observed in patients with RA aged 40 to >75 years.

Pediatric Patients:

Juvenile Idiopathic Arthritis:

- 4 years to 17 years of age: The adalimumab mean steady-state trough concentrations were 6.8 mcg/mL and 10.9 mcg/mL in patients weighing <30 kg receiving 20 mg adalimumab subcutaneously every other week as monotherapy or with concomitant MTX, respectively. The adalimumab mean steady-state trough concentrations were 6.6 mcg/mL and 8.1 mcg/mL in patients weighing ≥30 kg receiving 40 mg adalimumab subcutaneously every other week as monotherapy or with MTX concomitant treatment, respectively.
- 2 years to <4 years of age or 4 years of age and older weighing <15 kg: The adalimumab mean steady-state trough adalimumab concentrations were 6.0 mcg/mL and 7.9 mcg/mL in patients receiving adalimumab subcutaneously every other week as monotherapy or with MTX concomitant treatment, respectively.

Pediatric Hidradenitis Suppurativa: Adalimumab concentrations in adolescent patients with HS receiving the recommended dosage regimens are predicted to be similar to those observed in adult subjects with HS based on population pharmacokinetic modeling and simulation.

Pediatric Crohn's Disease:Adalimumab mean ± SD concentrations were 15.7±6.5 mcg/mL at Week 4 following 160 mg at Week 0 and 80 mg at Week 2, and 10.5±6.0 mcg/mL at Week 52 following 40 mg every other week dosing in patients weighing ≥ 40 kg. Adalimumab mean ± SD concentrations were 10.6±6.1 mcg/mL at Week 4 following dosing 80 mg at Week 0 and 40 mg at Week 2, and 6.9±3.6 mcg/mL at Week 52 following 20 mg every other week dosing in patients weighing < 40 kg.

Male and Female Patients: No gender-related pharmacokinetic differences were observed after correction for a patient’s body weight. Healthy subjects and patients with rheumatoid arthritis displayed similar adalimumab pharmacokinetics.

Patients with Renal or Hepatic Impairment: No pharmacokinetic data are available in patients with hepatic or renal impairment.

Rheumatoid factor or CRP concentrations: Minor increases in apparent clearance were predicted in RA patients receiving doses lower than the recommended dose and in RA patients with high rheumatoid factor or CRP concentrations. These increases are not likely to be clinically important.

Drug Interaction Studies:

Methotrexate: MTX reduced adalimumab apparent clearance after single and multiple dosing by 29% and 44% respectively, in patients with RA [see Drug Interactions (7.1)].

13 NONCLINICAL TOXICOLOGY

13.1 Carcinogenesis, Mutagenesis, Impairment of Fertility

Long-term animal studies of adalimumab products have not been conducted to evaluate the carcinogenic potential or its effect on fertility.

14 CLINICAL STUDIES

14.1 Clinical Studies in Rheumatoid Arthritis

The efficacy and safety of adalimumab were assessed in five randomized, double-blind studies in subjects ≥18 years of age with active rheumatoid arthritis (RA) diagnosed according to American College of Rheumatology (ACR) criteria. Subjects had at least 6 swollen and 9 tender joints. Adalimumab was administered subcutaneously in combination with methotrexate (MTX) (12.5 to 25 mg, Studies RA-I, RA-III and RA-V) or as monotherapy (Studies RA-II and RA-V) or with other disease-modifying anti-rheumatic drugs (DMARDs) (Study RA-IV).

Study RA-I evaluated 271 subjects who had failed therapy with at least one but no more than four DMARDs and had inadequate response to MTX. Doses of 20, 40 or 80 mg of adalimumab or placebo were given every other week for 24 weeks.

Study RA-II evaluated 544 subjects who had failed therapy with at least one DMARD. Doses of placebo, 20 mg or 40 mg of adalimumab were given as monotherapy every other week or weekly for 26 weeks.

Study RA-III evaluated 619 subjects who had an inadequate response to MTX. Subjects received placebo, 40 mg of adalimumab every other week with placebo injections on alternate weeks, or 20 mg of adalimumab weekly for up to 52 weeks. Study RA-III had an additional primary endpoint at 52 weeks of inhibition of disease progression (as detected by X-ray results). Upon completion of the first 52 weeks, 457 subjects enrolled in an open-label extension phase in which 40 mg of adalimumab was administered every other week for up to 5 years.

Study RA-IV assessed safety in 636 subjects who were either DMARD-naive or were permitted to remain on their pre-existing rheumatologic therapy provided that therapy was stable for a minimum of 28 days. Subjects were randomized to 40 mg of adalimumab or placebo every other week for 24 weeks.

Study RA-V evaluated 799 subjects with moderately to severely active RA of less than 3 years duration who were ≥18 years old and MTX naïve. Subjects were randomized to receive either MTX (optimized to 20 mg/week by Week 8), adalimumab 40 mg every other week or adalimumab/MTX combination therapy for 104 weeks. Subjects were evaluated for signs and symptoms, and for radiographic progression of joint damage. The median disease duration among subjects enrolled in the study was 5 months. The median MTX dose achieved was 20 mg.

Clinical Response

The percent of adalimumab treated subjects achieving ACR 20, 50 and 70 responses in Studies RA-II and III are shown in Table 3.

Table 3. ACR Responses in Studies RA-II and RA-III (Percent of Subjects)

 | Study RA-II Monotherapy (26 weeks) |  |  | Study RA-III Methotrexate Combination (24 and 52 weeks)
Response | Placebo | Adalimumab | Adalimumab | Placebo/MTX | Adalimumab/MTX
Response |  | 40 mg every; other week | 40 mg weekly |  | 40 mg every; other week
Response | N=110 | N=113 | N=103 | N=200 | N=207
ACR20
Month 6 | 19% | 46%* | 53%* | 30% | 63%*
Month 12 | NA | NA | NA | 24% | 59%*
ACR50
Month 6 | 8% | 22%* | 35%* | 10% | 39%*
Month 12 | NA | NA | NA | 10% | 42%*
ACR70
Month 6 | 2% | 12%* | 18%* | 3% | 21%*
Month 12 | NA | NA | NA | 5% | 23%*
* p<0.01, adalimumab vs. placebo

The results of Study RA-I were similar to Study RA-III; subjects receiving adalimumab 40 mg every other week in Study RA-I also achieved ACR 20, 50 and 70 response rates of 65%, 52% and 24%, respectively, compared to placebo responses of 13%, 7% and 3% respectively, at 6 months (p<0.01).

The results of the components of the ACR response criteria for Studies RA-II and RA-III are shown in Table 4. ACR response rates and improvement in all components of ACR response were maintained to Week 104. Over the 2 years in Study RA-III, 20% of adalimumab subjects receiving 40 mg every other week achieved a major clinical response, defined as maintenance of an ACR 70 response over a 6-month period. ACR responses were maintained in similar proportions of subjects for up to 5 years with continuous adalimumab treatment in the open-label portion of Study RA-III.

Table 4. Components of ACR Response in Studies RA-II and RA-III
 | Study RA-II |  |  |  | Study RA-III
Parameter (median) | Placebo N=110 |  | Adalimumaba N=113 |  | Placebo/MTX N=200 |  | Adalimumaba/MTX N=207
 | Baseline | Wk 26 | Baseline | Wk 26 | Baseline | Wk 24 | Baseline | Wk 24
Number of tender joints (0-68) | 35 | 26 | 31 | 16* | 26 | 15 | 24 | 8*
Number of swollen joints (0-66) | 19 | 16 | 18 | 10* | 17 | 11 | 18 | 5*
Physician global assessmentb | 7.0 | 6.1 | 6.6 | 3.7* | 6.3 | 3.5 | 6.5 | 2.0*
Patient global assessmentb | 7.5 | 6.3 | 7.5 | 4.5* | 5.4 | 3.9 | 5.2 | 2.0*
Painb | 7.3 | 6.1 | 7.3 | 4.1* | 6.0 | 3.8 | 5.8 | 2.1*
Disability index (HAQ)c | 2.0 | 1.9 | 1.9 | 1.5* | 1.5 | 1.3 | 1.5 | 0.8*
CRP (mg/dL) | 3.9 | 4.3 | 4.6 | 1.8* | 1.0 | 0.9 | 1.0 | 0.4*
a 40 mg adalimumab administered every other week.
b Visual analogue scale; 0 = best, 10 = worst.
c Disability Index of the Health Assessment Questionnaire; 0 = best, 3 = worst, measures the patient’s ability to perform the following: dress/groom, arise, eat, walk, reach, grip, maintain hygiene, and maintain daily activity.
* p<0.001, adalimumab vs. placebo, based on mean change from baseline.

The time course of ACR 20 response for Study RA-III is shown in Figure 1.

In Study RA-III, 85% of subjects with ACR 20 responses at Week 24 maintained the response at 52 weeks. The time course of ACR 20 response for Study RA-I and Study RA-II were similar.

Figure 1. Study RA-III ACR 20 Responses over 52 Weeks

In Study RA-IV, 53% of subjects treated with adalimumab 40 mg every other week plus standard of care had an ACR 20 response at Week 24 compared to 35% on placebo plus standard of care (p<0.001). No unique adverse reactions related to the combination of adalimumab and other DMARDs were observed.

In Study RA-V with MTX naïve subjects with recent onset RA, the combination treatment with adalimumab plus MTX led to greater percentages of subjects achieving ACR responses than either MTX monotherapy or adalimumab monotherapy at Week 52 and responses were sustained at Week 104 (see Table 5).

Table 5. ACR Response in Study RA-V (Percent of Subjects)
Response | MTXb N=257 | Adalimumabc N=274 | Adalimumab/MTX N=268
ACR 20 Week 52 Week 104 | 63% 56% | 54% 49% | 73% 69%
ACR 50 Week 52 Week 104 | 46% 43% | 41% 37% | 62% 59%
ACR 70 Week 52 Week 104 | 27% 28% | 26% 28% | 46% 47%
Major Clinical Response a | 28% | 25% | 49%
a Major clinical response is defined as achieving an ACR 70 response for a continuous six month period.
b p<0.05, adalimumab/MTX vs. MTX for ACR 20.
p<0.001, adalimumab/MTX vs. MTX for ACR 50 and 70, and Major Clinical Response.
c p<0.001, adalimumab/MTX vs. adalimumab.

At Week 52, all individual components of the ACR response criteria for Study RA-V improved in the adalimumab/MTX group and improvements were maintained to Week 104.

Radiographic Response

In Study RA-III, structural joint damage was assessed radiographically and expressed as change in Total Sharp Score (TSS) and its components, the erosion score and Joint Space Narrowing (JSN) score, at Month 12 compared to baseline. At baseline, the median TSS was approximately 55 in the placebo and 40 mg every other week groups. The results are shown in Table 6. Adalimumab/MTX treated subjects demonstrated less radiographic progression than subjects receiving MTX alone at 52 weeks.

Table 6. Radiographic Mean Changes Over 12 Months in Study RA-III
 | Placebo/MTX | Adalimumab/MTX 40 mg every other week | Placebo/MTX- Adalimumab/MTX (95% Confidence Interval*) | P-value**
Total Sharp score | 2.7 | 0.1 | 2.6 (1.4, 3.8) | <0.001
Erosion score | 1.6 | 0.0 | 1.6 (0.9, 2.2) | <0.001
JSN score | 1.0 | 0.1 | 0.9 (0.3, 1.4) | 0.002
*95% confidence intervals for the differences in change scores between MTX and adalimumab.
**Based on rank analysis.

In the open-label extension of Study RA-III, 77% of the original subjects treated with any dose of adalimumab were evaluated radiographically at 2 years. Subjects maintained inhibition of structural damage, as measured by the TSS. Fifty-four percent had no progression of structural damage as defined by a change in the TSS of zero or less. Fifty-five percent (55%) of subjects originally treated with 40 mg adalimumab every other week have been evaluated radiographically at 5 years. Subjects had continued inhibition of structural damage with 50% showing no progression of structural damage defined by a change in the TSS of zero or less.

In Study RA-V, structural joint damage was assessed as in Study RA-III. Greater inhibition of radiographic progression, as assessed by changes in TSS, erosion score and JSN was observed in the adalimumab/MTX combination group as compared to either the MTX or adalimumab monotherapy group at Week 52 as well as at Week 104 (see Table 7).

Table 7. Radiographic Mean Change* in Study RA-V
 |  | MTXa N=257 | Adalimumaba,b N=274 | Adalimumab/MTX N=268
52 Weeks | Total Sharp score | 5.7 (4.2, 7.3) | 3.0 (1.7, 4.3) | 1.3 (0.5, 2.1)
 | Erosion score | 3.7 (2.7, 4.8) | 1.7 (1.0, 2.4) | 0.8 (0.4, 1.2)
 | JSN score | 2.0 (1.2, 2.8) | 1.3 (0.5, 2.1) | 0.5 (0.0, 1.0)
104 Weeks | Total Sharp score | 10.4 (7.7, 13.2) | 5.5 (3.6, 7.4) | 1.9 (0.9, 2.9)
 | Erosion score | 6.4 (4.6, 8.2) | 3.0 (2.0, 4.0) | 1.0 (0.4, 1.6)
 | JSN score | 4.1 (2.7, 5.4) | 2.6 (1.5, 3.7) | 0.9 (0.3, 1.5)
* mean (95% confidence interval).
a p<0.001, adalimumab/MTX vs. MTX at 52 and 104 weeks and for adalimumab/MTX vs. adalimumab at 104 weeks.
b p<0.01, for adalimumab/MTX vs. adalimumab at 52 weeks.

Physical Function Response

In studies RA-I through IV, adalimumab showed significantly greater improvement than placebo in the disability index of Health Assessment Questionnaire (HAQ-DI) from baseline to the end of study, and significantly greater improvement than placebo in the health-outcomes as assessed by The Short Form Health Survey (SF 36). Improvement was seen in both the Physical Component Summary (PCS) and the Mental Component Summary (MCS).

In Study RA-III, the mean (95% CI) improvement in HAQ-DI from baseline at Week 52 was 0.60 (0.55, 0.65) for the adalimumab subjects and 0.25 (0.17, 0.33) for placebo/MTX (p<0.001) subjects. Sixty-three percent of adalimumab-treated subjects achieved a 0.5 or greater improvement in HAQ-DI at Week 52 in the double-blind portion of the study. Eighty-two percent of these subjects maintained that improvement through Week 104 and a similar proportion of subjects maintained this response through Week 260 (5 years) of open-label treatment. Mean improvement in the SF-36 was maintained through the end of measurement at Week 156 (3 years).

In Study RA-V, the HAQ-DI and the physical component of the SF-36 showed greater improvement (p<0.001) for the adalimumab/MTX combination therapy group versus either the MTX monotherapy or the adalimumab monotherapy group at Week 52, which was maintained through Week 104.

14.2 Clinical Studies in Juvenile Idiopathic Arthritis

The safety and efficacy of adalimumab was assessed in two studies (Studies JIA-I and JIA-II) in subjects with active polyarticular juvenile idiopathic arthritis (JIA).

Study JIA-I

The safety and efficacy of adalimumab were assessed in a multicenter, randomized, withdrawal, double-blind, parallel-group study in 171 subjects who were 4 to 17 years of age with polyarticular JIA. In the study, the subjects were stratified into two groups: MTX-treated or non-MTX-treated. All subjects had to show signs of active moderate or severe disease despite previous treatment with NSAIDs, analgesics, corticosteroids, or DMARDs. Subjects who received prior treatment with any biologic DMARDs were excluded from the study.

The study included four phases: an open-label lead in phase (OL-LI; 16 weeks), a double-blind randomized withdrawal phase (DB; 32 weeks), an open-label extension phase (OLE-BSA; up to 136 weeks), and an open-label fixed dose phase (OLE-FD; 16 weeks). In the first three phases of the study, adalimumab was administered based on body surface area at a dose of 24 mg/m^2 up to a maximum total body dose of 40 mg subcutaneously (SC) every other week. In the OLE-FD phase, the subjects were treated with 20 mg of adalimumab SC every other week if their weight was less than 30 kg and with 40 mg of adalimumab SC every other week if their weight was 30 kg or greater. Subjects remained on stable doses of NSAIDs and or prednisone (≤0.2 mg/kg/day or 10 mg/day maximum).

Subjects demonstrating a Pediatric ACR 30 response at the end of OL-LI phase were randomized into the double blind (DB) phase of the study and received either adalimumab or placebo every other week for 32 weeks or until disease flare. Disease flare was defined as a worsening of ≥30% from baseline in ≥3 of 6 Pediatric ACR core criteria, ≥2 active joints, and improvement of >30% in no more than 1 of the 6 criteria. After 32 weeks or at the time of disease flare during the DB phase, subjects were treated in the open-label extension phase based on the BSA regimen (OLE-BSA), before converting to a fixed dose regimen based on body weight (OLE-FD phase).

Study JIA-I Clinical Response

At the end of the 16-week OL-LI phase, 94% of the subjects in the MTX stratum and 74% of the subjects in the non-MTX stratum were Pediatric ACR 30 responders. In the DB phase significantly fewer subjects who received adalimumab experienced disease flare compared to placebo, both without MTX (43% vs. 71%) and with MTX (37% vs. 65%). More subjects treated with adalimumab continued to show pediatric ACR 30/50/70 responses at Week 48 compared to subjects treated with placebo. Pediatric ACR responses were maintained for up to two years in the OLE phase in subjects who received adalimumab throughout the study.

Study JIA-II

Adalimumab was assessed in an open-label, multicenter study in 32 subjects who were 2 to <4 years of age or 4 years of age and older weighing <15 kg with moderately to severely active polyarticular JIA. Most subjects (97%) received at least 24 weeks of adalimumab treatment dosed 24 mg/m^2 up to a maximum of 20 mg every other week as a single SC injection up to a maximum of 120 weeks duration. During the study, most subjects used concomitant MTX, with fewer reporting use of corticosteroids or NSAIDs. The primary objective of the study was evaluation of safety [see Adverse Reactions (6.1)].

14.3 Clinical Studies in Psoriatic Arthritis

The safety and efficacy of adalimumab was assessed in two randomized, double-blind, placebo-controlled studies in 413 subjects with psoriatic arthritis (PsA). Upon completion of both studies, 383 subjects enrolled in an open-label extension study, in which 40 mg adalimumab was administered every other week.

Study PsA-I enrolled 313 adult subjects with moderately to severely active PsA (>3 swollen and >3 tender joints) who had an inadequate response to NSAID therapy in one of the following forms: (1) distal interphalangeal (DIP) involvement (N=23); (2) polyarticular arthritis (absence of rheumatoid nodules and presence of plaque psoriasis) (N=210); (3) arthritis mutilans (N=1); (4) asymmetric PsA (N=77); or (5) AS-like (N=2). Subjects on MTX therapy (158 of 313 subjects) at enrollment (stable dose of ≤30 mg/week for >1 month) could continue MTX at the same dose. Doses of adalimumab 40 mg or placebo every other week were administered during the 24-week double-blind period of the study.

Compared to placebo, treatment with adalimumab resulted in improvements in the measures of disease activity (see Table 8 and Table 9). Among subjects with PsA who received adalimumab, the clinical responses were apparent in some subjects at the time of the first visit (two weeks) and were maintained up to 88 weeks in the ongoing open-label study. Similar responses were seen in subjects with each of the subtypes of psoriatic arthritis, although few subjects were enrolled with the arthritis mutilans and ankylosing spondylitis-like subtypes. Responses were similar in subjects who were or were not receiving concomitant MTX therapy at baseline.

Subjects with psoriatic involvement of at least three percent body surface area (BSA) were evaluated for Psoriatic Area and Severity Index (PASI) responses. At 24 weeks, the proportions of subjects achieving a 75% or 90% improvement in the PASI were 59% and 42% respectively, in the adalimumab group (N=69), compared to 1% and 0% respectively, in the placebo group (N=69) (p<0.001). PASI responses were apparent in some subjects at the time of the first visit (two weeks). Responses were similar in subjects who were or were not receiving concomitant MTX therapy at baseline.

Table 8. ACR Response in Study PsA-I (Percent of Subjects)
 | Placebo N=162 | Adalimumab* N=151
ACR 20 Week 12 Week 24 | 14% 15% | 58% 57%
ACR 50 Week 12 Week 24 | 4% 6% | 36% 39%
ACR 70 Week 12 Week 24 | 1% 1% | 20% 23%
* p<0.001 for all comparisons between adalimumab and placebo.

Table 9. Components of Disease Activity in Study PsA-I
 | Placebo N=162 |  | Adalimumab* N=151
Parameter: median | Baseline | 24 weeks | Baseline | 24 weeks
Number of tender jointsa | 23.0 | 17.0 | 20.0 | 5.0
Number of swollen jointsb | 11.0 | 9.0 | 11.0 | 3.0
Physician global assessmentc | 53.0 | 49.0 | 55.0 | 16.0
Patient global assessmentc | 49.5 | 49.0 | 48.0 | 20.0
Painc | 49.0 | 49.0 | 54.0 | 20.0
Disability index (HAQ) d | 1.0 | 0.9 | 1.0 | 0.4
CRP (mg/dL)e | 0.8 | 0.7 | 0.8 | 0.2
*p<0.001 for adalimumab vs. placebo comparisons based on median changes.
aScale 0-78.
bScale 0-76.
cVisual analog scale; 0=best, 100=worst.
dDisability Index of the Health Assessment Questionnaire; 0=best, 3=worst; measures the patient’s ability to perform the following: dress/groom, arise, eat, walk, reach, grip, maintain hygiene, and maintain daily activity.
eNormal range: 0-0.287 mg/dL.

Similar results were seen in an additional, 12-week study in 100 subjects with moderate to severe psoriatic arthritis who had suboptimal response to DMARD therapy as manifested by ≥3 tender joints and ≥3 swollen joints at enrollment.

Radiographic Response

Radiographic changes were assessed in the PsA studies. Radiographs of hands, wrists, and feet were obtained at baseline and Week 24 during the double-blind period when subjects were on adalimumab or placebo and at Week 48 when all subjects were on open-label adalimumab. A modified Total Sharp Score (mTSS), which included distal interphalangeal joints (i.e., not identical to the TSS used for rheumatoid arthritis), was used by readers blinded to treatment group to assess the radiographs.

Adalimumab-treated subjects demonstrated greater inhibition of radiographic progression compared to placebo-treated subjects and this effect was maintained at 48 weeks (see Table 10).

Table 10. Change in Modified Total Sharp Score in Psoriatic Arthritis
 | Placebo N=141 | Adalimumab N=133
 | Week 24 | Week 24 | Week 48
Baseline mean | 22.1 | 23.4 | 23.4
Mean Change ± SD | 0.9 ± 3.1 | -0.1 ± 1.7 | -0.2 ± 4.9*
* <0.001 for the difference between adalimumab, Week 48 and Placebo, Week 24 (primary analysis).

Physical Function Response

In Study PsA-I, physical function and disability were assessed using the HAQ Disability Index (HAQ-DI) and the SF-36 Health Survey. Subjects treated with 40 mg of adalimumab every other week showed greater improvement from baseline in the HAQ-DI score (mean decreases of 47% and 49% at Weeks 12 and 24 respectively) in comparison to placebo (mean decreases of 1% and 3% at Weeks 12 and 24 respectively). At Weeks 12 and 24, subjects treated with adalimumab showed greater improvement from baseline in the SF-36 Physical Component Summary score compared to subjects treated with placebo, and no worsening in the SF-36 Mental Component Summary score. Improvement in physical function based on the HAQ-DI was maintained for up to 84 weeks through the open-label portion of the study.

14.4 Clinical Studies in Ankylosing Spondylitis

The safety and efficacy of adalimumab 40 mg every other week was assessed in 315 adult subjects in a randomized, 24 week double-blind, placebo-controlled study in subjects with active ankylosing spondylitis (AS) who had an inadequate response to glucocorticoids, NSAIDs, analgesics, methotrexate or sulfasalazine. Active AS was defined as subjects who fulfilled at least two of the following three criteria: (1) a Bath AS disease activity index (BASDAI) score ≥4 cm, (2) a visual analog score (VAS) for total back pain ≥40 mm, and (3) morning stiffness ≥1 hour. The blinded period was followed by an open-label period during which subjects received adalimumab 40 mg every other week subcutaneously for up to an additional 28 weeks.

Improvement in measures of disease activity was first observed at Week 2 and maintained through 24 weeks as shown in Figure 2 and Table 11.

Responses of subjects with total spinal ankylosis (n=11) were similar to those without total ankylosis.

Figure 2. ASAS 20 Response By Visit, Study AS-I

At 12 weeks, the ASAS 20/50/70 responses were achieved by 58%, 38%, and 23%, respectively, of subjects receiving adalimumab, compared to 21%, 10%, and 5% respectively, of subjects receiving placebo (p <0.001). Similar responses were seen at Week 24 and were sustained in subjects receiving open-label adalimumab for up to 52 weeks.

A greater proportion of subjects treated with adalimumab (22%) achieved a low level of disease activity at 24 weeks (defined as a value <20 [on a scale of 0 to 100 mm] in each of the four ASAS response parameters) compared to subjects treated with placebo (6%).

Table 11. Components of Ankylosing Spondylitis Disease Activity
 | Placebo N=107 |  | Adalimumab N=208
 | Baseline mean | Week 24 mean | Baseline mean | Week 24 mean
ASAS 20 Response Criteria*
Patient’s Global Assessment of Disease Activitya* | 65 | 60 | 63 | 38
Total back pain* | 67 | 58 | 65 | 37
Inflammationb* | 6.7 | 5.6 | 6.7 | 3.6
BASFIc* | 56 | 51 | 52 | 34
BASDAId score* | 6.3 | 5.5 | 6.3 | 3.7
BASMIe score* | 4.2 | 4.1 | 3.8 | 3.3
Tragus to wall (cm) | 15.9 | 15.8 | 15.8 | 15.4
Lumbar flexion (cm) | 4.1 | 4.0 | 4.2 | 4.4
Cervical rotation (degrees) | 42.2 | 42.1 | 48.4 | 51.6
Lumbar side flexion (cm) | 8.9 | 9.0 | 9.7 | 11.7
Intermalleolar distance (cm) | 92.9 | 94.0 | 93.5 | 100.8
CRPf* | 2.2 | 2.0 | 1.8 | 0.6
aPercent of subjects with at least a 20% and 10-unit improvement measured on a Visual Analog Scale (VAS) with 0 = “none” and 100 = “severe”.
bmean of questions 5 and 6 of BASDAI (defined in ‘d’).
cBath Ankylosing Spondylitis Functional Index.
dBath Ankylosing Spondylitis Disease Activity Index.
eBath Ankylosing Spondylitis Metrology Index.
fC-Reactive Protein (mg/dL).
*statistically significant for comparisons between adalimumab and placebo at Week 24.

A second randomized, multicenter, double-blind, placebo-controlled study of 82 subjects with ankylosing spondylitis showed similar results.

Subjects treated with adalimumab achieved improvement from baseline in the Ankylosing Spondylitis Quality of Life Questionnaire (ASQoL) score (-3.6 vs. -1.1) and in the Short Form Health Survey (SF-36) Physical Component Summary (PCS) score (7.4 vs. 1.9) compared to placebo-treated subjects at Week 24.

14.5 Clinical Studies in Adults with Crohn’s Disease

The safety and efficacy of multiple doses of adalimumab were assessed in adult subjects with moderately to severely active Crohn’s disease, CD, (Crohn’s Disease Activity Index (CDAI) ≥220 and ≤450) in randomized, double-blind, placebo-controlled studies. Concomitant stable doses of aminosalicylates, corticosteroids, and/or immunomodulatory agents were permitted, and 79% of subjects continued to receive at least one of these medications.

Induction of clinical remission (defined as CDAI <150) was evaluated in two studies. In Study CD-I, 299 TNF-blocker naïve subjects were randomized to one of four treatment groups: the placebo group received placebo at Weeks 0 and 2, the 160/80 group received 160 mg adalimumab at Week 0 and 80 mg at Week 2, the 80/40 group received 80 mg at Week 0 and 40 mg at Week 2, and the 40/20 group received 40 mg at Week 0 and 20 mg at Week 2. Clinical results were assessed at Week 4.

In the second induction study, Study CD-II, 325 subjects who had lost response to, or were intolerant to, previous infliximab therapy were randomized to receive either 160 mg adalimumab at Week 0 and 80 mg at Week 2, or placebo at Weeks 0 and 2. Clinical results were assessed at Week 4.

Maintenance of clinical remission was evaluated in Study CD-III. In this study, 854 subjects with active disease received open-label adalimumab, 80 mg at Week 0 and 40 mg at Week 2. Subjects were then randomized at Week 4 to 40 mg adalimumab every other week, 40 mg adalimumab every week, or placebo. The total study duration was 56 weeks. Subjects in clinical response (decrease in CDAI ≥70) at Week 4 were stratified and analyzed separately from those not in clinical response at Week 4.

Induction of Clinical Remission

A greater percentage of the subjects treated with 160/80 mg adalimumab achieved induction of clinical remission versus placebo at Week 4 regardless of whether the subjects were TNF blocker naïve (CD-I), or had lost response to or were intolerant to infliximab (CD-II) (see Table 12).

Table 12. Induction of Clinical Remission in Studies CD-I and CD-II (Percent of Subjects)
 | CD-I |  | CD-II
 | Placebo N=74 | Adalimumab 160/80 mg N=76 | Placebo N=166 | Adalimumab 160/80 mg N=159
Week 4
Clinical remission | 12% | 36%* | 7% | 21%*
Clinical response | 34% | 58%** | 34% | 52%**
Clinical remission is CDAI score < 150; clinical response is decrease in CDAI of at least 70 points.
* p<0.001 for adalimumab vs. placebo pairwise comparison of proportions.
** p<0.01 for adalimumab vs. placebo pairwise comparison of proportions.

Maintenance of Clinical Remission

In Study CD-III at Week 4, 58% (499/854) of subjects were in clinical response and were assessed in the primary analysis. At Weeks 26 and 56, greater proportions of subjects who were in clinical response at Week 4 achieved clinical remission in the adalimumab 40 mg every other week maintenance group compared to subjects in the placebo maintenance group (see Table 13). The group that received adalimumab therapy every week did not demonstrate significantly higher remission rates compared to the group that received adalimumab every other week.

Table 13. Maintenance of Clinical Remission in CD-III (Percent of Subjects)
 | Placebo | 40 mg Adalimumab every other week
 | N=170 | N=172
Week 26
Clinical remission | 17% | 40%*
Clinical response | 28% | 54%*
Week 56
Clinical remission | 12% | 36%*
Clinical response | 18% | 43%*
Clinical remission is CDAI score <150; clinical response is decrease in CDAI of at least 70 points.
*p<0.001 for adalimumab vs. placebo pairwise comparisons of proportions.

Of those in response at Week 4 who attained remission during the study, subjects in the adalimumab every other week group maintained remission for a longer time than subjects in the placebo maintenance group. Among subjects who were not in response by Week 12, therapy continued beyond 12 weeks did not result in significantly more responses.

14.6 Clinical Studies in Pediatric Subjects with Crohn’s Disease

A randomized, double-blind, 52-week clinical study of 2 dose concentrations of adalimumab (Study PCD-I) was conducted in 192 pediatric subjects (6 to 17 years of age) with moderately to severely active Crohn’s disease (defined as Pediatric Crohn’s Disease Activity Index (PCDAI) score > 30). Enrolled subjects had over the previous two-year period an inadequate response to corticosteroids or an immunomodulator (i.e., azathioprine, 6-mercaptopurine, or methotrexate). Subjects who had previously received a TNF blocker were allowed to enroll if they had previously had loss of response or intolerance to that TNF blocker.

Subjects received open-label induction therapy at a dose based on their body weight (≥40 kg and <40 kg). Subjects weighing ≥40 kg received 160 mg (at Week 0) and 80 mg (at Week 2). Subjects weighing <40 kg received 80 mg (at Week 0) and 40 mg (at Week 2). At Week 4, subjects within each body weight category (≥40 kg and <40 kg) were randomized 1:1 to one of two maintenance dose regimens (high dose and low dose). The high dose was 40 mg every other week for subjects weighing ≥40 kg and 20 mg every other week for subjects weighing <40 kg. The low dose was 20 mg every other week for subjects weighing ≥40 kg and 10 mg every other week for subjects weighing <40 kg.

Concomitant stable dosages of corticosteroids (prednisone dosage ≤40 mg/day or equivalent) and immunomodulators (azathioprine, 6-mercaptopurine, or methotrexate) were permitted throughout the study.

At Week 12, subjects who experienced a disease flare (increase in PCDAI of ≥ 15 from Week 4 and absolute PCDAI > 30) or who were non-responders (did not achieve a decrease in the PCDAI of ≥ 15 from baseline for 2 consecutive visits at least 2 weeks apart) were allowed to dose-escalate (i.e., switch from blinded every other week dosing to blinded every week dosing); subjects who dose-escalated were considered treatment failures.

At baseline, 38% of subjects were receiving corticosteroids, and 62% of subjects were receiving an immunomodulator. Forty-four percent (44%) of subjects had previously lost response or were intolerant to a TNF blocker. The median baseline PCDAI score was 40.

Of the 192 subjects total, 188 subjects completed the 4 week induction period, 152 subjects completed 26 weeks of treatment, and 124 subjects completed 52 weeks of treatment. Fifty-one percent (51%) (48/95) of subjects in the low maintenance dose group dose-escalated, and 38% (35/93) of subjects in the high maintenance dose group dose-escalated.

At Week 4, 28% (52/188) of subjects were in clinical remission (defined as PCDAI ≤ 10).

The proportions of subjects in clinical remission (defined as PCDAI ≤ 10) and clinical response (defined as reduction in PCDAI of at least 15 points from baseline) were assessed at Weeks 26 and 52.

At both Weeks 26 and 52, the proportion of subjects in clinical remission and clinical response was numerically higher in the high dose group compared to the low dose group (Table 14). The recommended maintenance regimen is 20 mg every other week for subjects weighing < 40 kg and 40 mg every other week for subjects weighing ≥ 40 kg. Every week dosing is not the recommended maintenance dosing regimen [see Dosage and Administration (2.4)].

Table 14. Clinical Remission and Clinical Response in Study PCD-I

 | Low Maintenance Dose† (20 or 10 mg every other week) N = 95 | High Maintenance Dose# (40 or 20 mg every other week) N = 93
Week 26
Clinical Remission‡ | 28% | 39%
Clinical Response§ | 48% | 59%
Week 52
Clinical Remission‡ | 23% | 33%
Clinical Response§ | 28% | 42%
†The low maintenance dose was 20 mg every other week for subjects weighing ≥ 40 kg and 10 mg every other week for subjects weighing < 40 kg.
#The high maintenance dose was 40 mg every other week for subjects weighing ≥ 40 kg and 20 mg every other week for subjects weighing < 40 kg.
‡Clinical remission defined as PCDAI ≤ 10.
§Clinical response defined as reduction in PCDAI of at least 15 points from baseline.

14.7 Clinical Studies in Adults with Ulcerative Colitis

The safety and efficacy of adalimumab were assessed in adult subjects with moderately to severely active ulcerative colitis (Mayo score 6 to 12 on a 12-point scale, with an endoscopy subscore of 2 to 3 on a scale of 0 to 3) despite concurrent or prior treatment with immunosuppressants such as corticosteroids, azathioprine, or 6-MP in two randomized, double-blind, placebo-controlled clinical studies (Studies UC-I and UC-II). Both studies enrolled TNF-blocker naïve subjects, but Study UC-II also allowed entry of subjects who lost response to or were intolerant to TNF-blockers. Forty percent (40%) of subjects enrolled in Study UC-II had previously used another TNF-blocker.

Concomitant stable doses of aminosalicylates and immunosuppressants were permitted. In Studies UC-I and II, subjects were receiving aminosalicylates (69%), corticosteroids (59%) and/or azathioprine or 6-MP (37%) at baseline. In both studies, 92% of subjects received at least one of these medications.

Induction of clinical remission (defined as Mayo score ≤2 with no individual subscores >1) at Week 8 was evaluated in both studies. Clinical remission at Week 52 and sustained clinical remission (defined as clinical remission at both Weeks 8 and 52) were evaluated in Study UC-II.

In Study UC-I, 390 TNF-blocker naïve subjects were randomized to one of three treatment groups for the primary efficacy analysis. The placebo group received placebo at Weeks 0, 2, 4 and 6. The 160/80 group received 160 mg adalimumab at Week 0 and 80 mg at Week 2, and the 80/40 group received 80 mg adalimumab at Week 0 and 40 mg at Week 2. After Week 2, subjects in both adalimumab treatment groups received 40 mg every other week.

In Study UC-II, 518 subjects were randomized to receive either adalimumab 160 mg at Week 0, 80 mg at Week 2, and 40 mg every other week starting at Week 4 through Week 50, or placebo starting at Week 0 and every other week through Week 50. Corticosteroid taper was permitted starting at Week 8.

In both Studies UC-I and UC-II, a greater percentage of the subjects treated with 160/80 mg of adalimumab compared to subjects treated with placebo achieved induction of clinical remission. In Study UC-II, a greater percentage of the subjects treated with 160/80 mg of adalimumab compared to subjects treated with placebo achieved sustained clinical remission (clinical remission at both Weeks 8 and 52) (Table 15).

Table 15. Induction of Clinical Remission in Studies UC-I and UC-II and Sustained Clinical Remission in Study UC-II (Percent of Subjects)

 | Study UC-I |  |  | Study UC-II
 | Placebo N=130 | Adalimumab 160/80 mg N=130 | Treatment Difference (95% CI) | Placebo N=246 | Adalimumab 160/80 mg N=248 | Treatment Difference (95% CI)
Induction of Clinical Remission (Clinical Remission at Week 8) | 9.2% | 18.5% | 9.3%* (0.9%, 17.6%) | 9.3% | 16.5% | 7.2%* (1.2%, 12.9%)
Sustained Clinical Remission (Clinical Remission at both Weeks 8 and 52) | N/A | N/A | N/A | 4.1% | 8.5% | 4.4%* (0.1%, 8.6%)
Clinical remission is defined as Mayo score ≤2 with no individual subscores >1.
CI=Confidence interval.
* p<0.05 for adalimumab vs. placebo pairwise comparison of proportions.

In Study UC-I, there was no statistically significant difference in clinical remission observed between the adalimumab 80/40 mg group and the placebo group at Week 8.

In Study UC-II, 17.3% (43/248) in the adalimumab group were in clinical remission at Week 52 compared to 8.5% (21/246) in the placebo group (treatment difference: 8.8%; 95% confidence interval (CI): [2.8%, 14.5%]; p<0.05).

In the subgroup of subjects in Study UC-II with prior TNF-blocker use, the treatment difference for induction of clinical remission appeared to be lower than that seen in the whole study population, and the treatment differences for sustained clinical remission and clinical remission at Week 52 appeared to be similar to those seen in the whole study population. The subgroup of subjects with prior TNF -blocker use achieved induction of clinical remission at 9% (9/98) in the adalimumab group versus 7% (7/101) in the placebo group, and sustained clinical remission at 5% (5/98) in the adalimumab group versus 1% (1/101) in the placebo group. In the subgroup of subjects with prior TNF-blocker use, 10% (10/98) were in clinical remission at Week 52 in the adalimumab group versus 3% (3/101) in the placebo group.

14.9 Clinical Studies in Plaque Psoriasis

The safety and efficacy of adalimumab were assessed in randomized, double-blind, placebo-controlled studies in 1696 adult subjects with moderate to severe chronic plaque psoriasis (Ps) who were candidates for systemic therapy or phototherapy.

Study Ps-I evaluated 1212 subjects with chronic Ps with ≥10% body surface area (BSA) involvement, Physician’s Global Assessment (PGA) of at least moderate disease severity, and Psoriasis Area and Severity Index (PASI) ≥12 within three treatment periods. In period A, subjects received placebo or adalimumab at an initial dose of 80 mg at Week 0 followed by a dose of 40 mg every other week starting at Week 1. After 16 weeks of therapy, subjects who achieved at least a PASI 75 response at Week 16, defined as a PASI score improvement of at least 75% relative to baseline, entered period B and received open-label 40 mg adalimumab every other week. After 17 weeks of open label therapy, subjects who maintained at least a PASI 75 response at Week 33 and were originally randomized to active therapy in period A were re-randomized in period C to receive 40 mg adalimumab every other week or placebo for an additional 19 weeks. Across all treatment groups the mean baseline PASI score was 19 and the baseline Physician’s Global Assessment score ranged from “moderate” (53%) to “severe” (41%) to “very severe” (6%).

Study Ps-II evaluated 99 subjects randomized to adalimumab and 48 subjects randomized to placebo with chronic plaque psoriasis with ≥10% BSA involvement and PASI ≥12. Subjects received placebo, or an initial dose of 80 mg adalimumab at Week 0 followed by 40 mg every other week starting at Week 1 for 16 weeks. Across all treatment groups the mean baseline PASI score was 21 and the baseline PGA score ranged from “moderate” (41%) to “severe” (51%) to “very severe” (8%).

Studies Ps-I and II evaluated the proportion of subjects who achieved “clear” or “minimal” disease on the 6-point PGA scale and the proportion of subjects who achieved a reduction in PASI score of at least 75% (PASI 75) from baseline at Week 16 (see Table 16 and 17).

Additionally, Study Ps-I evaluated the proportion of subjects who maintained a PGA of “clear” or “minimal” disease or a PASI 75 response after Week 33 and on or before Week 52.

Table 16. Efficacy Results at 16 Weeks in Study Ps-I Number of Subjects (%)
 | Adalimumab 40 mg every other week | Placebo
 | N = 814 | N = 398
PGA: Clear or minimal* | 506 (62%) | 17 (4%)
PASI 75 | 578 (71%) | 26 (7%)
* Clear = no plaque elevation, no scale, plus or minus hyperpigmentation or diffuse pink or red coloration.
Minimal = possible but difficult to ascertain whether there is slight elevation of plaque above normal skin, plus or minus surface dryness with some white coloration, plus or minus up to red coloration.

Table 17. Efficacy Results at 16 Weeks in Study Ps-II Number of Subjects (%)
 | Adalimumab 40 mg every other week | Placebo
 | N = 99 | N = 48
PGA: Clear or minimal* | 70 (71%) | 5 (10%)
PASI 75 | 77 (78%) | 9 (19%)
* Clear = no plaque elevation, no scale, plus or minus hyperpigmentation or diffuse pink or red coloration.
Minimal = possible but difficult to ascertain whether there is slight elevation of plaque above normal skin, plus or minus surface dryness with some white coloration, plus or minus up to red coloration.

Additionally, in Study Ps-I, subjects on adalimumab who maintained a PASI 75 were re-randomized to adalimumab (N = 250) or placebo (N = 240) at Week 33. After 52 weeks of treatment with adalimumab, more subjects on adalimumab maintained efficacy when compared to subjects who were re-randomized to placebo based on maintenance of PGA of “clear” or “minimal” disease (68% vs. 28%) or a PASI 75 (79% vs. 43%).

A total of 347 stable responders participated in a withdrawal and retreatment evaluation in an open-label extension study. Median time to relapse (decline to PGA “moderate” or worse) was approximately 5 months. During the withdrawal period, no subject experienced transformation to either pustular or erythrodermic psoriasis. A total of 178 subjects who relapsed re-initiated treatment with 80 mg of adalimumab, then 40 mg every other week beginning at Week 1. At Week 16, 69% (123/178) of subjects had a response of PGA “clear” or “minimal”.

A randomized, double-blind study (Study Ps-III) compared the efficacy and safety of adalimumab versus placebo in 217 adult subjects. Subjects in the study had to have chronic plaque psoriasis of at least moderate severity on the PGA scale, fingernail involvement of at least moderate severity on a 5-point Physician’s Global Assessment of Fingernail Psoriasis (PGA-F) scale, a Modified Nail Psoriasis Severity Index (mNAPSI) score for the target-fingernail of ≥ 8, and either a BSA involvement of at least 10 % or a BSA involvement of at least 5 % with a total mNAPSI score for all fingernails of ≥ 20. Subjects received an initial dose of 80 mg adalimumab followed by 40 mg every other week (starting one week after the initial dose) or placebo for 26 weeks followed by open-label adalimumab treatment for an additional 26 weeks. This study evaluated the proportion of subjects who achieved “clear” or “minimal” assessment with at least a 2-grade improvement on the PGA-F scale and the proportion of subjects who achieved at least a 75 % improvement from baseline in the mNAPSI score (mNAPSI 75) at Week 26.

At Week 26, a higher proportion of subjects in the adalimumab group than in the placebo group achieved the PGA-F endpoint. Furthermore, a higher proportion of subjects in the adalimumab group than in the placebo group achieved mNAPSI 75 at Week 26 (see Table 18).

Table 18. Efficacy Results at 26 Weeks

Endpoint | Adalimumab 40 mg; every other week*; N=109 | Placebo; N=108
PGA-F: ≥ 2-grade improvement and clear or minimal | 49 % | 7 %
mNAPSI 75 | 47 % | 3 %
* Subjects received 80 mg of adalimumab at Week 0, followed by 40 mg every other week starting at Week 1.

Nail pain was also evaluated and improvement in nail pain was observed in Study Ps-III.

14.10 Clinical Studies in Hidradenitis Suppurativa

Two randomized, double-blind, placebo-controlled studies (Studies HS-I and II) evaluated the safety and efficacy of adalimumab in a total of 633 adult subjects with moderate to severe hidradenitis suppurativa (HS) with Hurley Stage II or III disease and with at least 3 abscesses or inflammatory nodules. In both studies, subjects received placebo or adalimumab at an initial dose of 160 mg at Week 0, 80 mg at Week 2, and 40 mg every week starting at Week 4 and continued through Week 11. Subjects used topical antiseptic wash daily. Concomitant oral antibiotic use was allowed in Study HS-II.

Both studies evaluated Hidradenitis Suppurativa Clinical Response (HiSCR) at Week 12. HiSCR was defined as at least a 50% reduction in total abscess and inflammatory nodule count with no increase in abscess count and no increase in draining fistula count relative to baseline (see Table 19). Reduction in HS-related skin pain was assessed using a Numeric Rating Scale in subjects who entered the study with an initial baseline score of 3 or greater on a 11-point scale.

In both studies, a higher proportion of adalimumab-than placebo-treated subjects achieved HiSCR (see Table 19).

Table 19. Efficacy Results at 12 Weeks in Subjects with Moderate to Severe Hidradenitis Suppurativa

 | HS Study I |  | HS Study II*
 | Placebo | Adalimumab 40 mg Weekly | Placebo | Adalimumab 40 mg Weekly
Hidradenitis Suppurativa Clinical Response (HiSCR) | N = 154; 40 (26 %) | N = 153; 64 (42 %) | N = 163; 45 (28 %) | N = 163; 96 (59 %)
* 19.3 % of subjects in Study HS-II continued baseline oral antibiotic therapy during the study.

In both studies, from Week 12 to Week 35 (Period B), subjects who had received adalimumab were re-randomized to 1 of 3 treatment groups (adalimumab 40 mg every week, adalimumab 40 mg every other week, or placebo). Subjects who had been randomized to placebo were assigned to receive adalimumab 40 mg every week (Study HS-I) or placebo (Study HS-II).

During Period B, flare of HS, defined as ≥25% increase from baseline in abscesses and inflammatory nodule counts and with a minimum of 2 additional lesions, was documented in 22 (22%) of the 100 subjects who were withdrawn from adalimumab treatment following the primary efficacy timepoint in two studies.

14.11 Clinical Studies in Adults with Uveitis

The safety and efficacy of adalimumab were assessed in adult subjects with non-infectious intermediate, posterior and panuveitis excluding subjects with isolated anterior uveitis, in two randomized, double-masked, placebo-controlled studies (UV I and II). Subjects received placebo or adalimumab at an initial dose of 80 mg followed by 40 mg every other week starting one week after the initial dose. The primary efficacy endpoint in both studies was ´time to treatment failure´.

Treatment failure was a multi-component outcome defined as the development of new inflammatory chorioretinal and/or inflammatory retinal vascular lesions, an increase in anterior chamber (AC) cell grade or vitreous haze (VH) grade or a decrease in best corrected visual acuity (BCVA).

Study UV I evaluated 217 subjects with active uveitis while being treated with corticosteroids (oral prednisone at a dose of 10 to 60 mg/day). All subjects received a standardized dose of prednisone 60 mg/day at study entry followed by a mandatory taper schedule, with complete corticosteroid discontinuation by Week 15.

Study UV II evaluated 226 subjects with inactive uveitis while being treated with corticosteroids (oral prednisone 10 to 35 mg/day) at baseline to control their disease. Subjects subsequently underwent a mandatory taper schedule, with complete corticosteroid discontinuation by Week 19.

Clinical Response

Results from both studies demonstrated statistically significant reduction of the risk of treatment failure in subjects treated with adalimumab versus subjects receiving placebo. In both studies, all components of the primary endpoint contributed cumulatively to the overall difference between adalimumab and placebo groups (Table 20).

Table 20. Time to Treatment Failure in Studies UV I and UV II

 | UV I |  |  | UV II
 | Placebo; (N = 107) | Adalimumab; (N = 110) | HR; [95% CI]a | Placebo; (N = 111) | Adalimumab; (N = 115) | HR; [95% CI]a
Failureb n (%) | 84 (78.5) | 60 (54.5) | 0.50; [0.36, 0.70] | 61 (55.0) | 45 (39.1) | 0.57; [0.39, 0.84]
Median Time; to Failure (Months); [95% CI] | 3.0; [2.7, 3.7] | 5.6; [3.9, 9.2] | N/A | 8.3; [4.8, 12.0] | NEc | N/A
a HR of adalimumab versus placebo from proportional hazards regression with treatment as factor.
b Treatment failure at or after Week 6 in Study UV I, or at or after Week 2 in Study UV II, was counted as event. Subjects who discontinued the study were censored at the time of dropping out.
c NE = not estimable. Fewer than half of at-risk subjects had an event.

Figure 3: Kaplan-Meier Curves Summarizing Time to Treatment Failure on or after Week 6 (Study UV I) or Week 2 (Study UV II)

Study UV I

Study UV II

Note: P# = Placebo (Number of Events/Number at Risk); A# = Adalimumab (Number of Events/Number at Risk).

14.12 Clinical Studies in Pediatric Subjects with Uveitis

The safety and efficacy of adalimumab were assessed in a randomized, double-masked, placebo-controlled study of 90 pediatric subjects from 2 to < 18 years of age with active JIA-associated non-infectious uveitis (PUV-I). Subjects received either placebo or 20 mg adalimumab (if < 30 kg) or 40 mg adalimumab (if ≥ 30 kg) every other week in combination with a dose of methotrexate. Concomitant dosages of corticosteroids were permitted at study entry followed by a mandatory reduction in topical corticosteroids within 3 months.

The primary endpoint was ‘time to treatment failure’. The criteria determining treatment failure were worsening or sustained non-improvement in ocular inflammation, or worsening of ocular co-morbidities.

Clinical Response

Adalimumab significantly decreased the risk of treatment failure by 75% relative to placebo (HR = 0.25 [95% CI: 0.12, 0.49]) (Table 21).

Table 21. Analysis Results of Time to Treatment Failure (Study PUV-I)

 | Placebo; (N=30) | Adalimumab (N=60) | HR (95% CI)ª
Failure (n[%]) | 18 (60%) | 16 (26.7%) | 0.25 (0.12, 0.49)
Median Time to Failure (Weeks) (95% CI)ᵇ | 24.1 (12.4, 81.0) | NEᶜ

a HR of adalimumab versus placebo from proportional hazards regression with treatment as factor.

b Estimated based on Kaplan-Meier curve.

c NE = not estimable. Fewer than half of at-risk subjects had an event.

Figure 4: Kaplan-Meier Curves Summarizing Time to Treatment Failure (Study PUV-I)

Study PUV-I

Note: P = Placebo (Number at Risk); H = Adalimumab (Number at Risk).

15 REFERENCES

1. National Cancer Institute. Surveillance, Epidemiology, and End Results Database (SEER) Program. SEER Incidence Crude Rates, 17 Registries, 2000-2007.

16 HOW SUPPLIED/STORAGE AND HANDLING

Adalimumab-adaz single-dose prefilled Sensoready Pen, Adalimumab-adaz single-dose prefilled syringe with BD UltraSafe Passive™ Needle Guard and add-on finger flange and Adalimumab-adaz single-dose prefilled syringe.

Adalimumab-adaz injection is supplied as a preservative-free, sterile, clear and colorless or slightly yellowish solution for subcutaneous administration. The following packaging configurations are available.

80 mg/0.8 mL single-dose prefilled Sensoready Pen with a fixed 29 gauge, ½ inch needle | Carton of 2 | NDC 61314-325-20
80 mg/0.8 mL single-dose prefilled Sensoready Pen with a fixed 29 gauge, ½ inch needle | Crohn’s disease and Ulcerative Colitis or Hidradenitis Suppurativa Starter Package Carton of 3 | NDC 61314-349-36
80 mg/0.8 mL and 40 mg/0.4 mL single-dose prefilled Sensoready Pens with fixed 29 gauge, ½ inch needle each | Plaque Psoriasis, Uveitis or Adolescent Hidradenitis Suppurativa Starter Package; Carton of 3; (1x 80 mg/0.8 mL, 2x 40 mg/0.4 mL) | NDC 61314-345-36
80 mg/0.8 mL and 40 mg/0.4 mL single-dose prefilled Sensoready Pens with fixed 29 gauge, ½ inch needle each | Crohn’s Disease, Ulcerative Colitis or Hidradenitis Suppurativa Starter Package Carton of 4; (3x 80 mg/0.8 mL, 1x 40 mg/0.4 mL) | NDC 61314-359-84
80 mg/0.8 mL single-dose prefilled syringe with a fixed 29 gauge, ½ inch needle and with BD UltraSafe Passive™ Needle Guard | Carton of 2 | NDC 61314-325-64
80 mg/0.8 mL single-dose prefilled syringe with a fixed 29 gauge, ½ inch needle and with BD UltraSafe Passive™ Needle Guard | Starter Pack for Pediatric Crohn’s Disease; Carton of 3 | NDC 61314-420-68
80 mg/0.8 mL and 40 mg/0.4 mL single-dose prefilled syringe with a fixed 29 gauge, ½ inch needle and with BD UltraSafe Passive™ Needle Guard | Starter Pack for Pediatric Crohn’s Disease; Carton of 2 | NDC 61314-430-64
40 mg/0.4 mL single-dose prefilled syringe with a fixed 29 gauge, ½ inch needle and with BD UltraSafe Passive™ Needle Guard | Carton of 2 | NDC 61314-327-64
40 mg/0.4 mL single-dose prefilled Sensoready Pen with a fixed 29 gauge, ½ inch needle | Carton of 2 | NDC 61314-327-20
40 mg/0.4 mL single-dose prefilled Sensoready Pen with a fixed 29 gauge, ½ inch needle | Carton of 4 | NDC 61314-327-84
20 mg/0.2 mL single-dose prefilled syringe with a fixed 29 gauge, ½ inch needle | Carton of 2 | NDC 61314-332-64
10 mg/0.1 mL single-dose prefilled syringe with a fixed 29 gauge, ½ inch needle | Carton of 2 | NDC 61314-391-64

Prefilled syringes and injection devices are not made with natural rubber latex.

Storage and Handling

Do not use beyond the expiration date on the container. Adalimumab-adaz must be refrigerated at 36°F to 46°F (2°C to 8°C). DO NOT FREEZE. Do not use if frozen even if it has been thawed.

Store in original carton until time of administration to protect from light.

Do not store Adalimumab-adaz in extreme heat or cold.

Adalimumab-adaz single-dose prefilled syringe with BD UltraSafe Passive™ Needle Guard (40 mg/0.4 mL, 80 mg/0.8 mL), Adalimumab-adaz single-dose prefilled Sensoready Pen (40 mg/0.4 mL, 80 mg/0.8 mL) and Adalimumab-adaz single-dose prefilled syringe (10 mg/0.1 mL, 20 mg/0.2 mL):

If needed, for example when traveling, Adalimumab-adaz may be stored at room temperature up to a maximum of 77°F (25°C) for a period of up to 14 days, with protection from light. Adalimumab-adaz should be discarded if not used within the 14-day period. Record the date when Adalimumab-adaz is first removed from the refrigerator in the spaces provided on the carton.

17 PATIENT COUNSELING INFORMATION

Advise the patient or caregiver to read the FDA-approved patient labeling (Medication Guide and Instructions for Use).

Infections

Inform patients that Adalimumab-adaz may lower the ability of their immune system to fight infections. Instruct patients of the importance of contacting their doctor if they develop any symptoms of infection, including tuberculosis, invasive fungal infections, and reactivation of hepatitis B virus infections [see Warnings and Precautions (5.1, 5.2, 5.4)].

Malignancies

Counsel patients about the risk of malignancies while receiving Adalimumab-adaz [see Warnings and Precautions (5.2)].

Hypersensitivity Reactions

Advise patients to seek immediate medical attention if they experience any symptoms of severe hypersensitivity reactions.

Other Medical Conditions

Advise patients to report any signs of new or worsening medical conditions such as congestive heart failure, neurological disease, autoimmune disorders, or cytopenias. Advise patients to report any symptoms suggestive of a cytopenia such as bruising, bleeding, or persistent fever [see Warnings and Precautions (5.5, 5.6, 5.8, 5.9)].

Instructions on Injection Technique

Inform patients that the first injection is to be performed under the supervision of a qualified health care professional. If a patient or caregiver is to administer Adalimumab-adaz, instruct them in injection techniques and assess their ability to inject subcutaneously to ensure the proper administration of Adalimumab-adaz [see Instructions for Use].

For patients who will use the Adalimumab-adaz single-dose prefilled Sensoready Pen, tell them that they:

- will hear 2 loud clicks. The 1st click indicates that the injection has started. Several seconds later a 2nd click will indicate that the injection is almost finished.
- must keep holding the Adalimumab-adaz single-dose prefilled Sensoready Pen firmly against their skin until they see a green indicator fill the window and stop moving.

Instruct patients to dispose of their used syringes or used Sensoready Pens in an FDA-cleared sharps disposal container immediately after use. Instruct patients not to dispose of syringes or pens in their household trash. Instruct patients that if they do not have an FDA-cleared sharps disposal container, they may use a household container that is made of a heavy-duty plastic, can be closed with a tight-fitting and puncture-resistant lid without sharps being able to come out, upright and stable during use, leak-resistant, and properly labeled to warn of hazardous waste inside the container.

Instruct patients that when their sharps disposal container is almost full, they will need to follow their community guidelines for the correct way to dispose of their sharps disposal container. Instruct patients that there may be state or local laws regarding disposal of used needles and syringes. Refer patients to the FDA’s website at http://www.fda.gov/safesharpsdisposal for more information about safe sharps disposal, and for specific information about sharps disposal in the state that they live in.

Instruct patients not to dispose of their used sharps disposal container in their household trash unless their community guidelines permit this. Instruct patients not to recycle their used sharps disposal container.

Manufactured by:

Sandoz Inc.

Princeton, NJ 08540

US License No. 2003

All third party trademarks are the property of their respective owners.

MEDICATION GUIDE

ADALIMUMAB-ADAZ (ada-LIM-u-mab adaz)

injection, for subcutaneous use

This product is HYRIMOZ® (adalimumab-adaz).

Read the Medication Guide that comes with Adalimumab-adaz before you start taking it and each time you get a refill. There may be new information. This Medication Guide does not take the place of talking with your doctor about your medical condition or treatment.

What is the most important information I should know about Adalimumab-adaz?

Adalimumab-adaz is a medicine that affects your immune system. Adalimumab-adaz can lower the ability of your immune system to fight infections.

Serious infections have happened in people taking adalimumab products. These serious infections include tuberculosis (TB) and infections caused by viruses, fungi or bacteria that have spread throughout the body. Some people have died from these infections.

- Your doctor should test you for TB before starting Adalimumab-adaz.
- Your doctor should check you closely for signs and symptoms of TB during treatment with Adalimumab-adaz.

You should not start taking Adalimumab-adaz if you have any kind of infection unless your doctor says it is okay.

Before starting Adalimumab-adaz, tell your doctor if you:

- think you have an infection or have symptoms of an infection such as:
  - fever, sweats or chills
  - warm, red, or painful skin or sores on your body
  - muscle aches
  - diarrhea or stomach pain
  - cough
  - burning when you urinate or urinate more often than normal
  - shortness of breath
  - feel very tired
  - blood in phlegm
  - weight loss
- are being treated for an infection.
- get a lot of infections or have infections that keep coming back.
- have diabetes.
- have TB, or have been in close contact with someone with TB.
- were born in, lived in, or traveled to countries where there is more risk for getting TB. Ask your doctor if you are not sure.
- live or have lived in certain parts of the country (such as the Ohio and Mississippi River valleys) where there is an increased risk for getting certain kinds of fungal infections (histoplasmosis, coccidioidomycosis, or blastomycosis). These infections may happen or become more severe if you use Adalimumab-adaz. Ask your doctor if you do not know if you have lived in an area where these infections are common.
- have or have had hepatitis B.
- use the medicine ORENCIA (abatacept), KINERET (anakinra), RITUXAN (rituximab), IMURAN (azathioprine), or PURINETHOL (6–mercaptopurine, 6-MP).
- are scheduled to have major surgery.

After starting Adalimumab-adaz, call your doctor right away if you have an infection, or any sign of an infection. Adalimumab-adaz can make you more likely to get infections or make any infection that you may have worse.

Cancer

- For children and adults taking Tumor Necrosis Factor (TNF)-blockers, including Adalimumab-adaz, the chances of getting cancer may increase.
- There have been cases of unusual cancers in children, teenagers, and young adults using TNF-blockers.
- People with rheumatoid arthritis (RA), especially more serious RA, may have a higher chance for getting a kind of cancer called lymphoma.
- If you use TNF-blockers including Adalimumab-adaz your chance of getting two types of skin cancer may increase (basal cell cancer and squamous cell cancer of the skin). These types of cancer are generally not life-threatening if treated. Tell your doctor if you have a bump or open sore that does not heal.
- Some people receiving TNF-blockers including Adalimumab-adaz developed a rare type of cancer called hepatosplenic T-cell lymphoma. This type of cancer often results in death. Most of these people were male teenagers or young men. Also, most people were being treated for Crohn’s disease or ulcerative colitis with another medicine called IMURAN (azathioprine) or PURINETHOL (6-mercaptopurine, 6–MP).

What is Adalimumab-adaz?

Adalimumab-adaz is a medicine called a Tumor Necrosis Factor (TNF)-blocker. Adalimumab-adaz is used:

- To reduce the signs and symptoms of:
  - moderate to severe rheumatoid arthritis (RA) in adults. Adalimumab-adaz can be used alone, with methotrexate, or with certain other medicines.
  - moderate to severe polyarticular juvenile idiopathic arthritis (JIA) in children 2 years and older. Adalimumab-adaz can be used alone or with methotrexate.
  - psoriatic arthritis (PsA) in adults. Adalimumab-adaz can be used alone or with certain other medicines.
  - ankylosing spondylitis (AS) in adults.
  - moderate to severe hidradenitis suppurativa (HS) in people 12 years and older.
- To treat moderate to severe Crohn’s disease (CD) in adults and children 6 years of age and older.
- To treat moderate to severe ulcerative colitis (UC) in adults. It is not known if adalimumab products are effective in people who stopped responding to or could not tolerate TNF-blocker medicines.
- To treat moderate to severe chronic (lasting a long time) plaque psoriasis (Ps) in adults who have the condition in many areas of their body and who may benefit from taking injections or pills (systemic therapy) or phototherapy (treatment using ultraviolet light alone or with pills).
- To treat non-infectious intermediate, posterior, and panuveitis in adults and children 2 years of age and older.

What should I tell my doctor before taking Adalimumab-adaz?

Adalimumab-adaz may not be right for you. Before starting Adalimumab-adaz, tell your doctor about all of your medical conditions, including if you:

- have an infection. See “What is the most important information I should know about Adalimumab-adaz?”
- have or have had cancer.
- have any numbness or tingling or have a disease that affects your nervous system such as multiple sclerosis or Guillain-Barré syndrome.
- have or had heart failure.
- have recently received or are scheduled to receive a vaccine. You may receive vaccines, except for live vaccines while using Adalimumab-adaz. Children should be brought up to date with all vaccines before starting Adalimumab-adaz.
- are allergic to Adalimumab-adaz or to any of its ingredients. See the end of this Medication Guide for a list of ingredients in Adalimumab-adaz.
- are pregnant or plan to become pregnant, breastfeeding or plan to breastfeed. You and your doctor should decide if you should take Adalimumab-adaz while you are pregnant or breastfeeding.
- have a baby and you were using Adalimumab-adaz during your pregnancy. Tell your baby’s doctor before your baby receives any vaccines.

Tell your doctor about all the medicines you take, including prescription and over-the-counter medicines, vitamins, and herbal supplements.

Especially tell your doctor if you use:

- ORENCIA (abatacept), KINERET (anakinra), REMICADE (infliximab), ENBREL (etanercept), CIMZIA (certolizumab pegol) or SIMPONI (golimumab), because you should not use Adalimumab-adaz while you are also using one of these medicines.
- RITUXAN (rituximab). Your doctor may not want to give you Adalimumab-adaz if you have received RITUXAN (rituximab) recently.
- IMURAN (azathioprine) or PURINETHOL (6–mercaptopurine, 6-MP).

Keep a list of your medicines with you to show your doctor and pharmacist each time you get a new medicine.

How should I take Adalimumab-adaz?

- Adalimumab-adaz is given by an injection under the skin. Your doctor will tell you how often to take an injection of Adalimumab-adaz. This is based on your condition to be treated. Do not inject Adalimumab-adaz more often than you were prescribed.
- See the Instructions for Use inside the carton for complete instructions for the right way to prepare and inject Adalimumab-adaz.
- Make sure you have been shown how to inject Adalimumab-adaz before you do it yourself. You can call your doctor or 1-800-525-8747 if you have any questions about giving yourself an injection. Someone you know can also help you with your injection after they have been shown how to prepare and inject Adalimumab-adaz.
- Do not try to inject Adalimumab-adaz yourself until you have been shown the right way to give the injections. If your doctor decides that you or a caregiver may be able to give your injections of Adalimumab-adaz at home, you should receive training on the right way to prepare and inject Adalimumab-adaz.
- Do not miss any doses of Adalimumab-adaz unless your doctor says it is okay. If you forget to take Adalimumab-adaz, inject a dose as soon as you remember. Then, take your next dose at your regular scheduled time. This will put you back on schedule. In case you are not sure when to inject Adalimumab-adaz, call your doctor or pharmacist.
- If you take more Adalimumab-adaz than you were told to take, call your doctor.

What are the possible side effects of Adalimumab-adaz?

Adalimumab-adaz can cause serious side effects, including:

See “What is the most important information I should know about Adalimumab-adaz?”

- Serious Infections. Your doctor will examine you for TB and perform a test to see if you have TB. If your doctor feels that you are at risk for TB, you may be treated with medicine for TB before you begin treatment with Adalimumab-adaz and during treatment with Adalimumab-adaz. Even if your TB test is negative your doctor should carefully monitor you for TB infections while you are taking Adalimumab-adaz. People who had a negative TB skin test before receiving adalimumab products have developed active TB. Tell your doctor if you have any of the following symptoms while taking or after taking Adalimumab-adaz:
- cough that does not go away
- weight loss
- low grade fever
- loss of body fat and muscle (wasting)
- Hepatitis B infection in people who carry the virus in their blood. If you are a carrier of the hepatitis B virus (a virus that affects the liver), the virus can become active while you use Adalimumab-adaz. Your doctor should do blood tests before you start treatment, while you are using Adalimumab-adaz, and for several months after you stop treatment with Adalimumab-adaz. Tell your doctor if you have any of the following symptoms of a possible hepatitis B infection:
- muscle aches
- clay-colored bowel movements
- feel very tired
- fever
- dark urine
- chills
- skin or eyes look yellow
- stomach discomfort
- little or no appetite
- skin rash
- vomiting
- Allergic reactions. Allergic reactions can happen in people who use Adalimumab-adaz. Call your doctor or get medical help right away if you have any of these symptoms of a serious allergic reaction:
- hives
- swelling of your face, eyes, lips or mouth
- trouble breathing
- Nervous system problems. Signs and symptoms of a nervous system problem include: numbness or tingling, problems with your vision, weakness in your arms or legs, and dizziness.
- Blood problems. Your body may not make enough of the blood cells that help fight infections or help to stop bleeding. Symptoms include a fever that does not go away, bruising or bleeding very easily, or looking very pale.
- New heart failure or worsening of heart failure you already have. Call your doctor right away if you get new worsening symptoms of heart failure while taking Adalimumab-adaz, including:
- shortness of breath
- swelling of your ankles or feet
- sudden weight gain
- Immune reactions including a lupus-like syndrome. Symptoms include chest discomfort or pain that does not go away, shortness of breath, joint pain, or a rash on your cheeks or arms that gets worse in the sun. Symptoms may improve when you stop Adalimumab-adaz.
- Liver problems. Liver problems can happen in people who use TNF-blocker medicines. These problems can lead to liver failure and death. Call your doctor right away if you have any of these symptoms:
- feel very tired
- skin or eyes look yellow
- poor appetite or vomiting
- pain on the right side of your stomach (abdomen)
- Psoriasis. Some people using adalimumab products had new psoriasis or worsening of psoriasis they already had. Tell your doctor if you develop red scaly patches or raised bumps that are filled with pus. Your doctor may decide to stop your treatment with Adalimumab-adaz.

Call your doctor or get medical care right away if you develop any of the above symptoms. Your treatment with Adalimumab-adaz may be stopped.

The most common side effects of Adalimumab-adaz include:

- injection site reactions: redness, rash, swelling, itching, or bruising. These symptoms usually will go away within a few days. Call your doctor right away if you have pain, redness or swelling around the injection site that does not go away within a few days or gets worse.
- upper respiratory infections (including sinus infections).
- headaches.
- rash.

These are not all the possible side effects with Adalimumab-adaz. Tell your doctor if you have any side effect that bothers you or that does not go away. Ask your doctor or pharmacist for more information.

Call your doctor for medical advice about side effects. You may report side effects to FDA at 1-800-FDA-1088.

How should I store Adalimumab-adaz?

- Store Adalimumab-adaz in the refrigerator at 36ºF to 46ºF (2ºC to 8ºC). Store Adalimumab-adaz in the original carton until use to protect it from light.
- Do not freeze Adalimumab-adaz. Do not use Adalimumab-adaz if frozen, even if it has been thawed.
- Refrigerated Adalimumab-adaz may be used until the expiration date printed on the carton of the Adalimumab-adaz single-dose prefilled Sensoready Pen or the Adalimumab-adaz single-dose prefilled syringe. Do not use Adalimumab-adaz after the expiration date.
- If needed, for example when you are traveling, you may also store the Adalimumab-adaz 80 mg/0.8 mL single-dose prefilled Sensoready Pen or single-dose prefilled syringe with BD UltraSafe Passive Needle Guard, Adalimumab-adaz 40 mg/0.4 mL single-dose prefilled Sensoready Pen or single-dose prefilled syringe with BD UltraSafe Passive Needle Guard, Adalimumab-adaz 20 mg/0.2 mL single-dose prefilled syringe and Adalimumab-adaz 10 mg/0.1 mL single-dose prefilled syringe for up to 14 days. Store Adalimumab-adaz in the original carton until use to protect it from light. Throw away Adalimumab-adaz 80 mg/0.8 mL, 40 mg/0.4 mL, 20 mg/0.2 mL and 10 mg/0.1 mL if it has been kept at room temperature and not been used within 14 days.
- Record the date you first remove Adalimumab-adaz from the refrigerator in the spaces provided on the carton.
- Do not store Adalimumab-adaz in extreme heat or cold.
- The solution should be clear and colorless or slightly yellowish. Do not use Adalimumab-adaz if the solution is cloudy, discolored, or has flakes or particles in it.
- Do not drop or crush Adalimumab-adaz. The prefilled syringe is glass.
- The prefilled syringes and injection devices are not made with natural rubber latex.

Keep Adalimumab-adaz, injection supplies, and all other medicines out of the reach of children.

General information about the safe and effective use of Adalimumab-adaz.

Medicines are sometimes prescribed for purposes other than those listed in a Medication Guide. Do not use Adalimumab-adaz for a condition for which it was not prescribed. Do not give Adalimumab-adaz to other people, even if they have the same condition. It may harm them.

This Medication Guide summarizes the most important information about Adalimumab-adaz. If you would like more information, talk with your doctor. You can ask your pharmacist or doctor for information about Adalimumab-adaz that is written for health professionals.

What are the ingredients in Adalimumab-adaz?

Active ingredient: adalimumab-adaz

Adalimumab-adaz single-dose prefilled Sensoready Pen 80 mg/0.8 mL and 40 mg/0.4 mL, Adalimumab-adaz single-dose prefilled syringe with BD UltraSafe Passive Needle Guard 80 mg/0.8 mL and 40 mg/0.4 mL and Adalimumab-adaz single-dose prefilled syringe 20 mg/0.2 mL and 10 mg/0.1 mL:

Inactive ingredients: adipic acid, mannitol, polysorbate 80, and Water for Injection. Hydrochloric acid and sodium hydroxide are added as necessary to adjust pH.

Manufactured by:

Sandoz Inc.

Princeton, NJ 08540

All third party trademarks are the property of their respective owners.

For more information go to www.HYRIMOZ.com or you can enroll in a patient support program by calling 1-800-525-8747.

US License No. 2003

This Medication Guide has been approved by the U.S. Food and Drug Administration. Revised: 10/2025

INSTRUCTIONS FOR USE

Adalimumab-adaz (ada-LIM-u-mab adaz)

80 mg/0.8 mL, 40 mg/0.4 mL

Single-dose prefilled Syringe with BD UltraSafe Passive™ Needle Guard and finger flange

injection, for subcutaneous use

This product is HYRIMOZ® (adalimumab-adaz).

To help avoid possible infections and to ensure that you use Adalimumab-adaz correctly, it is important that you follow these instructions.

Be sure that you read, understand, and follow this Instructions for Use before injecting Adalimumab-adaz. Your doctor should show you how to prepare and inject Adalimumab-adaz properly using the Adalimumab-adaz single-dose prefilled syringe before you use it for the first time. Talk to your doctor if you have any questions.

Figure A: Adalimumab-adaz prefilled syringe with BD UltraSafe Passive™ Needle Guard and finger flange

It is important that you:

- do not use the prefilled syringe if the seals of the blister are broken, as it may not be safe for you to use.
- do not open the outer box until you are ready to use the prefilled syringe.
- never leave the prefilled syringe unattended where others might misuse it.
- do not remove the needle cap until just before you give the injection.
- be careful not to touch the needle guard wings before use. Touching them may cause the needle guard to be activated too early.
- do not remove the finger flange before the injection.
- inject Adalimumab-adaz 15 to 30 minutes after taking it out of the refrigerator for a more comfortable injection.
- throw away (dispose of) the used prefilled syringe right away after use. Do not re-use a prefilled syringe. See “4. Disposing of used prefilled syringes” at the end of this Instructions for Use.

Note: Adalimumab-adaz prefilled syringe and injection device are not made with natural rubber latex

How should you store Adalimumab-adaz single-dose prefilled syringe?

- Store your outer carton of prefilled syringes in a refrigerator between 36°F to 46°F (2°C to 8°C).
- If needed, for example if you are traveling, you may store the prefilled syringe at room temperature up to 77°F (25°C) for up to 14 days.
- Throw away the prefilled syringe that has been stored at room temperature after 14 days.
- Record the date you first remove Adalimumab-adaz from the refrigerator in the spaces provided on the carton.
- Keep your prefilled syringes in the original carton until ready to use to protect from light.
- Do not store your prefilled syringes in extreme heat or cold.
- Do not freeze your prefilled syringes.
- Do not drop or crush Adalimumab-adaz. The prefilled syringe is glass.

Keep Adalimumab-adaz and all medicines out of the reach of children.

What do you need for your injection?

Included in your prefilled syringe carton are:

- Adalimumab-adaz prefilled syringes (see Figure A). Each prefilled syringe contains 80 mg/0.8 mL or 40 mg/0.4 mL of adalimumab-adaz.

Not included in your Adalimumab-adaz prefilled syringe carton are:

- Alcohol wipe
- Cotton ball or gauze
- Sharps disposal container. See “4. Disposing of used prefilled syringes” at the end of this Instructions for Use.
- Adhesive bandage

Figure B: items not included in the carton

Before your injection

Figure C: needle guard is not activated – the single-dose prefilled syringe is ready for use

Figure D: needle guard is activated – do not use

- In Figure C the needle guard is not activated.
- The prefilled syringe is ready for use (see Figure C).

- In Figure D the needle guard of your prefilled syringe is activated.
- Do not use the prefilled syringe (see Figure D).

Preparing the prefilled syringe

- For a more comfortable injection, take the carton containing the prefilled syringe out of the refrigerator and leave it unopened on your work surface for about 15 to 30 minutes to allow it to reach room temperature. Do not try to warm the prefilled syringe by using a heat source such as hot water or a microwave.
- Take the prefilled syringe out of the blister. The solution should be clear and colorless or slightly yellowish. Do not use a prefilled syringe if the solution is cloudy, discolored, or has flakes or particles in it. If you are not sure what color the solution should be, contact your pharmacist for help.
- Do not use the prefilled syringe if it is broken or the needle guard is activated. Return the prefilled syringe and the package it came in to the pharmacy.
- Look at the expiration date (EXP) on your prefilled syringe. Do not use your prefilled syringe if the expiration date has passed.

Contact your pharmacist if:

- you are unsure about the color of the solution in the prefilled syringe.
- the prefilled syringe is broken or the needle guard is activated.
- the expiration date has passed.
1. Choosing your injection site
- The recommended injection site is the front of your thighs. You may also use the lower abdomen, but not the area 2 inches (5 cm) around your navel (belly button) (see Figure E).
- Choose a different site each time you give yourself an injection.
- Do not inject into areas where the skin is tender, bruised, red, scaly, or hard. Avoid areas with scars or stretch marks. If you have psoriasis, you should not inject directly into areas with psoriasis plaques.

Figure E: choose your injection site

2. Cleaning your injection site

- Wash your hands well with soap and water.
- Using a circular motion, clean the injection site with an alcohol wipe. Let it dry before injecting (see Figure F). Do not fan or blow on the cleaned area.
- Do not touch the cleaned area before injecting.

Figure F: clean your injection site

3. Giving your injection

- Carefully pull the needle cap straight off to remove it from the prefilled syringe (see Figure G).
- Throw away (discard) the needle cap.
- You may see a drop of liquid at the end of the needle. This is normal.

Figure G: pull the needle cap off

- Gently pinch the skin at the injection site (see Figure H).
- Insert the needle into your skin as shown.
- Push the needle all the way in to ensure that the medicine can be fully given.

Figure H: insert the needle

- Hold the single-dose prefilled syringe as shown (see Figure I).
- Slowly press down on the plunger as far as it will go, so that the plunger head is completely between the needle guard wings.
- Continue to press fully on the plunger while you hold the syringe in place for 5 seconds.

Figure I: hold the syringe

- Keep the plunger fully pressed down while you carefully lift the needle straight out from the injection site and let go of your skin (see Figure J).

Figure J: lift the needle straight out

- Slowly release the plunger and allow the needle safety guard to automatically cover the exposed needle (see Figure K).
- There may be a small amount of blood at the injection site. You can press a cotton ball or gauze onto the injection site and hold it for 10 seconds. Do not rub the injection site. You may cover the injection site with a small adhesive bandage, if needed.

Figure K: slowly release the plunger

4. Disposing of used prefilled syringes
2. Put your used prefilled syringe in an FDA-cleared sharps disposal container right away after use (see Figure L). Do not throw away (dispose of) any prefilled syringes in your household trash.
3. If you do not have an FDA-cleared sharps disposal container, you may use a household container that is:
  - made of a heavy-duty plastic,
  - can be closed with a tight-fitting, puncture-resistant lid, without sharps being able to come out,
  - upright and stable during use,
  - leak resistant, and
  - properly labeled to warn of hazardous waste inside the container.
4. When your sharps container is almost full, you will need to follow your community guidelines, for the right way to dispose of your sharps disposal container. There may be a state or local laws about how you should throw away used syringes, needles and prefilled syringe. For more information about safe sharps disposal, and for specific information about sharps disposal, in the state that you live in, go to the FDA’s website at: www.fda.gov/safesharpsdisposal
5. Do not dispose your used sharps disposal container in your household trash unless your community guidelines permit this. Do not recycle your used sharps disposal container.

Figure L: dispose of your used prefilled syringe

Manufactured by:
Sandoz Inc.
Princeton, NJ 08540

US License No. 2003

All third party trademarks are the property of their respective owners.

This Instructions for Use has been approved by the U.S. Food and Drug Administration. Revised: 06/2024

INSTRUCTIONS FOR USE

Adalimumab-adaz (ada-LIM-u-mab adaz)

80 mg/0.8 mL, 40 mg/0.4 mL

Single-dose prefilled Sensoready® Pen

injection, for subcutaneous use

This product is HYRIMOZ® (adalimumab-adaz).

To help avoid possible infections and to ensure that you use Adalimumab-adaz correctly, it is important that you follow these instructions.

Be sure that you read, understand, and follow this Instructions for Use before injecting Adalimumab-adaz. Your doctor should show you how to prepare and inject Adalimumab-adaz properly using the Adalimumab-adaz single-dose prefilled Sensoready Pen before you use it for the first time. Talk to your doctor if you have any questions.

Figure A: Adalimumab-adaz Sensoready Pen parts

In Figure A, the Sensoready Pen is shown with the cap removed. Do not remove the cap until you are ready to inject.

It is important that you:

- do not use the Sensoready Pen if either the seal on the outer carton or the safety seal on the Pen is broken.
- keep your Sensoready Pen in the sealed outer carton until you are ready to use it.
- do not use your Sensoready Pen, if you dropped it, it looks damaged, or if you dropped it with the cap removed.
- inject Adalimumab-adaz 15 to 30 minutes after taking it out of the refrigerator for a more comfortable injection.
- throw away (dispose of) the used Sensoready Pen right away after use. Do not reuse a Sensoready Pen. See “8. Disposing of used Sensoready Pens” at the end of this Instructions for Use.

Note: Adalimumab-adaz prefilled syringe and injection device are not made with natural rubber latex

How should you store your Sensoready Pen?

- Store your Sensoready Pen carton in a refrigerator between 36°F to 46°F (2°C to 8°C).
- If needed, for example if you are traveling, you may store your Sensoready Pen at room temperature at up to 77°F (25°C) for up to 14 days.
- Throw away any Sensoready Pen that has been stored at room temperature after 14 days.
- Record the date you first remove Adalimumab-adaz from the refrigerator in the spaces provided on the carton.
- Keep your Sensoready Pen in the original carton until ready to use to protect from light.
- Do not store your Sensoready Pen in extreme heat or cold.
- Do not freeze your Sensoready Pen.
- Do not drop or crush Adalimumab-adaz. Your Sensoready Pen contains glass.

Keep Adalimumab-adaz and all medicines out of the reach of children.

What do you need for your injection?

Included in your Sensoready Pen carton are:

- Adalimumab-adaz prefilled Sensoready Pens (see Figure A). Each Sensoready Pen contains 80 mg/0.8 mL or 40 mg/0.4 mL of adalimumab-adaz.

Not included in your Sensoready Pen carton are:

- Alcohol wipe
- Cotton ball or gauze
- Sharps disposal container. See “8. Disposing of used Sensoready Pens” at the end of this Instructions for Use.
- Adhesive bandage

Figure B: items not included in the carton

Before your injection

Preparing the Sensoready Pen

- For a more comfortable injection, take your Sensoready pen out of the refrigerator 15 to 30 minutes before injecting Adalimumab-adaz to allow it to reach room temperature. Do not try to warm the prefilled pen by using a heat source such as hot water or a microwave.
- Look through the viewing window. The solution should be clear and colorless or slightly yellowish. Do not use your Sensoready Pen if the solution is cloudy, discolored, or has flakes or particles in it. You may see small air bubbles, which is normal. If you are not sure what color the solution should be, then contact your pharmacist for help.
- Look at the expiration date (EXP) on your Sensoready Pen (see Figure C). Do not use your Sensoready Pen if the expiration date has passed.
- Do not use if the safety seal has been broken.

Figure C: safety checks before injection

Contact your pharmacist if:

- you are unsure about the color of the solution in the Sensoready Pen.
- the safety seal of your Sensoready Pen is broken.
- the expiration date has passed.
1. Choosing your injection site
- The recommended injection site is the front of your thighs. You may also use the lower abdomen, but not the area 2 inches (5 cm) around your navel (belly button) (see Figure D).
- Choose a different site each time you give yourself an injection.
- Do not inject into areas where the skin is tender, bruised, red, scaly, or hard. Avoid areas with scars or stretch marks.
- If you have psoriasis, you should not inject directly into areas with psoriasis plaques.

Figure D: choose your injection site

2. Cleaning your injection site
2. Wash your hands well with soap and water.
3. Using a circular motion, clean the injection site with an alcohol wipe. Let it dry before injecting (see Figure E). Do not fan or blow on the cleaned area.
4. Do not touch the cleaned area before injecting.

Figure E: clean your injection site

3. Removing the cap of your Sensoready Pen
2. Only remove the cap when you are ready to use the Sensoready Pen.
3. Twist off the cap in the direction of the arrows (see Figure F).
4. After removed, throw away the cap. Do not try to re-attach the cap.
5. Use your Sensoready Pen within 5 minutes of removing the cap.
6. You may see a few drops of medicine come out of the needle. This is normal.

Figure F: remove the cap

4. Holding your Sensoready Pen
2. Hold your Sensoready Pen at 90 degrees to the cleaned injection site (see Figure G).

Figure G: hold your pen

Your injection

You must read this before injecting
During the injection you will hear 2 loud clicks:

- The first click indicates that the injection has started.
- Several seconds later a second click will indicate that the injection is almost finished.

You must keep holding your Sensoready Pen firmly against your skin until you see a green indicator fill the window and stop moving.

5. Starting your injection
2. Press your Sensoready Pen firmly against the skin to start the injection (see Figure H).
3. The first click indicates the injection has started.
4. Keep holding your Sensoready Pen firmly against your skin.
5. The green indicator shows the progress of the injection.

Figure H: start your injection

6. Completing your injection
2. Listen for the second click. This indicates the injection is almost complete.
3. Check that the green indicator fills the window and has stopped moving (see Figure I).
4. The Sensoready Pen can now be removed.

Figure I: complete your injection

After your injection

7. Check that the green indicator fills the window (see Figure J)
2. This means the medicine has been delivered. Contact your doctor if the green indicator is not visible.
3. There may be a small amount of blood at the injection site. You can press a cotton ball or gauze over the injection site and hold it for 10 seconds. Do not rub the injection site. You may cover the injection site with a small adhesive bandage, if needed.

Figure J: check the green indicator

8. Disposing of used Sensoready Pens
2. Put your used Sensoready Pen in an FDA-cleared sharps disposal container right away after use (see Figure K). Do not throw away (dispose of) any Sensoready Pens in your household trash.
3. If you do not have an FDA-cleared sharps disposal container, you may use a household container that is:
  - made of a heavy-duty plastic,
  - can be closed with a tight-fitting, puncture-resistant lid, without sharps being able to come out,
  - upright and stable during use,
  - leak resistant, and
  - properly labeled to warn of hazardous waste inside the container.
4. When your sharps container is almost full, you will need to follow your community guidelines, for the right way to dispose of your sharps disposal container. There may be state or local laws about how you should throw away used syringes, needles and pens. For more information about safe sharps disposal, and for specific information about sharps disposal, in the state that you live in, go to the FDA’s website at:
www.fda.gov/safesharpsdisposal
6. Do not dispose your used sharps disposal container in your household trash unless your community guidelines permit this. Do not recycle your used sharps disposal container.

Figure K: dispose of your used pen

Manufactured by:
Sandoz Inc.
Princeton, NJ 08540

US License No. 2003

All third party trademarks are the property of their respective owners.

This Instructions for Use has been approved by the U.S. Food and Drug Administration Revised: 06/2024

INSTRUCTIONS FOR USE

Adalimumab-adaz (ada-LIM-u-mab adaz)

10 mg/0.1 mL, 20 mg/0.2 mL

Single-dose prefilled Syringe

injection, for subcutaneous use

This product is HYRIMOZ® (adalimumab-adaz).

To help avoid possible infections and to ensure that you use Adalimumab-adaz correctly, it is important that you follow these instructions.

Be sure that you read, understand, and follow this Instructions for Use before injecting Adalimumab-adaz. Your doctor should show you how to prepare and inject Adalimumab-adaz properly using the Adalimumab-adaz single-dose prefilled syringe before you use it for the first time. Talk to your doctor if you have any questions.

Figure A: Adalimumab-adaz prefilled syringe.

It is important that you:

- do not use the prefilled syringe if the seal on the outer carton is broken, as it may not be safe to use.
- do not open the inner carton until you are ready to use the Adalimumab-adaz prefilled syringe.
- never leave the prefilled syringe unattended where others might misuse it.
- if you drop your syringe, do not use it if it looks damaged, or if you dropped it with the needle cap removed.
- do not remove the needle cap until just before you give the injection. Inject Adalimumab-adaz 15 to 30 minutes after taking it out of the refrigerator for a more comfortable injection.
- throw away the used syringe right away after use. Do not re-use a syringe. See “4. Disposing of used prefilled syringes” at the end of these Instructions for Use.
- do not remove the finger grip before the injection.
- consult your doctor or nurse for advice on an appropriate injection site and injection technique if you are underweight or if you are injecting a child.

Note: Adalimumab-adaz prefilled syringe is not made with natural rubber latex.

How should you store Adalimumab-adaz single-dose prefilled syringe?

- Store the Adalimumab-adaz prefilled syringe in the original carton to protect it from light.
- Store your outer carton of prefilled syringe in a refrigerator between 36°F and 46°F (2°C and 8°C).
- If needed, for example if you are traveling, you may store the prefilled syringe at room temperature up to 77°F (25°C) for up to 14 days.
- Throw away the prefilled syringe that has been stored at room temperature after 14 days.
- Do not store your prefilled syringe in extreme heat or cold.
- Do not freeze your prefilled syringe.
- Record the date you first remove Adalimumab-adaz from the refrigerator in the spaces provided on the carton.
- Do not drop or crush Adalimumab-adaz. The prefilled syringe is glass.

Keep Adalimumab-adaz and all medicines out of the reach of children.

What do you need for your injection?

Included in your prefilled syringe carton are:

- Adalimumab-adaz prefilled syringes (see Figure A). Each prefilled syringe contains 10 mg/0.1 mL or 20 mg/0.2 mL of adalimumab-adaz.

Not included in your Adalimumab-adaz prefilled syringe carton are (see Figure B):

- Alcohol wipe
- Cotton ball or gauze
- Sharps disposal container. See “4. Disposing of used prefilled syringes” at the end of this Instructions for Use.
- Adhesive bandage

Figure B: items not included in the carton.

Preparing the prefilled syringe

- For a more comfortable injection, take the outer carton containing the prefilled syringe out of the refrigerator and leave it unopened on your work surface for about 15 to 30 minutes to allow it to reach room temperature.
- Do not try to warm the prefilled syringe by using a heat source such as hot water or microwave.
- Remove the prefilled syringe out of the carton box and inspect it. The solution should be clear and colorless or slightly yellowish. Do not use a prefilled syringe if the solution is cloudy, discolored, or has flakes or particles in it. If you are not sure what color the solution should be, contact your pharmacist for help.
- Do not use the prefilled syringe if it is broken. Return the prefilled syringe and the package it came in to the pharmacy.
- Look at the expiration date (EXP) on your prefilled syringe. Do not use your prefilled syringe if the expiration date has passed.

Contact your pharmacist if:

- you are unsure about the color of the solution in the prefilled syringe.
- the prefilled syringe is broken.
- the expiration date has passed.

1. Choosing your injection site
2. The recommended injection site is the front of the thighs. You may also use the lower abdomen, but not the area 2 inches (5 cm) around the navel (belly button) (see Figure C).
3. Choose a different site each time you give an injection.
4. Do not inject into areas where the skin is tender, bruised, red, scaly, or hard. Avoid areas with scars or stretch marks.
5. If you have psoriasis, you should not inject directly into areas with psoriasis plaques.

Figure C: choose your injection site.

2. Cleaning your injection site
2. When you are ready to use the prefilled syringe, wash your hands thoroughly with soap and water.
3. Using a circular motion, clean the injection site with an alcohol wipe. Let it dry before injecting (see Figure D).
4. Do not touch the cleaned area again before giving the injection. Allow the skin to dry before injecting. Do not fan or blow on the clean area.

Figure D: clean your injection site.

3. Giving your injection
2. Carefully pull the needle cap straight off to remove it from the prefilled syringe (see Figure E).
3. Throw away (discard) the needle cap.
4. You may see a drop of liquid at the end of the needle. This is normal.

Figure E: pull the needle cap off.

- Gently pinch the skin at the injection site (see Figure F).
- Insert the needle into the skin at a 45-degree angle, as shown
(see Figure F).

Figure F: pinch the skin and insert the needle.

- Hold the single-dose prefilled syringe as shown (see Figure G).
- Slowly press down on the plunger as far as it will go.
- Continue to press fully on the plunger while you hold the syringe in place for 5 seconds.
- Carefully lift the needle straight out from the injection site and let go of the skin. There may be a small amount of blood at the injection site. You can press a cotton ball or gauze onto the injection site and hold it for 10 seconds. Do not rub the injection site. You may cover the injection site with a small adhesive bandage, if needed.

Figure G: press down the plunger.

4. Disposing of used prefilled syringes
2. Put the used prefilled syringe in an FDA-cleared sharps disposal container right away after use (see Figure H). Do not throw away (dispose of) any prefilled syringes in your household trash.
3. If you do not have an FDA-cleared sharps disposal container, you may use a household container that is:
4. made of a heavy-duty plastic,
5. can be closed with a tight-fitting, puncture-resistant lid, without sharps being able to come out,
6. upright and stable during use,
7. leak resistant, and
8. Properly labeled to warn of hazardous waste inside the container.
9. When your sharps container is almost full, you will need to follow your community guidelines, for the right way to dispose of your sharps disposal container. There may be state or local laws about how you should throw away used syringes, needles and prefilled syringes. For more information about safe sharps disposal, and for specific information about sharps disposal, in the state that you live in, go to the FDA’s website at: www.fda.gov/safesharpsdisposal
10. Do not dispose your used sharps disposal container in your household trash unless your community guidelines permit this. Do not recycle your used sharps disposal container.

Figure H: dispose of the used prefilled syringe.

Manufactured by:

Sandoz Inc.

Princeton, NJ 08540

US License No. 2003

All third party trademarks are the property of their respective owners.

This Instructions for Use has been approved by the U.S. Food and Drug Administration Revised: 06/2024

Principal Display Panel

NDC 61314-327-20

Rx only

Adalimumab-adaz Injection

40 mg/0.4 mL

For Subcutaneous Use Only

2 Single-Dose Prefilled Sensoready® Pens

This product is Hyrimoz®

SANDOZ

Principal Display Panel

NDC 61314-327-64

Rx only

Adalimumab-adaz Injection

40 mg/0.4 mL

For Subcutaneous Use Only

2 Single-Dose Prefilled Syringes with needle guard

This product is Hyrimoz®

SANDOZ

Principal Display Panel

NDC 61314-332-64

Rx only

Adalimumab-adaz Injection

20 mg/0.2 mL

For Subcutaneous Use Only

2 Single-Dose Prefilled Syringes

This product is Hyrimoz®

SANDOZ

Principal Display Panel

NDC 61314-325-20

Rx only

Adalimumab-adaz Injection

80 mg/0.8 mL

For Subcutaneous Use Only

2 Single-Dose Prefilled Sensoready® Pens

This product is Hyrimoz®

SANDOZ

Principal Display Panel

NDC 61314-391-64

Rx Only

Adalimumab-adaz Injection

10 mg/0.1 mL

For Subcutaneous Use Only

2 Single-Dose Prefilled Syringes

This product is Hyrimoz®

SANDOZ